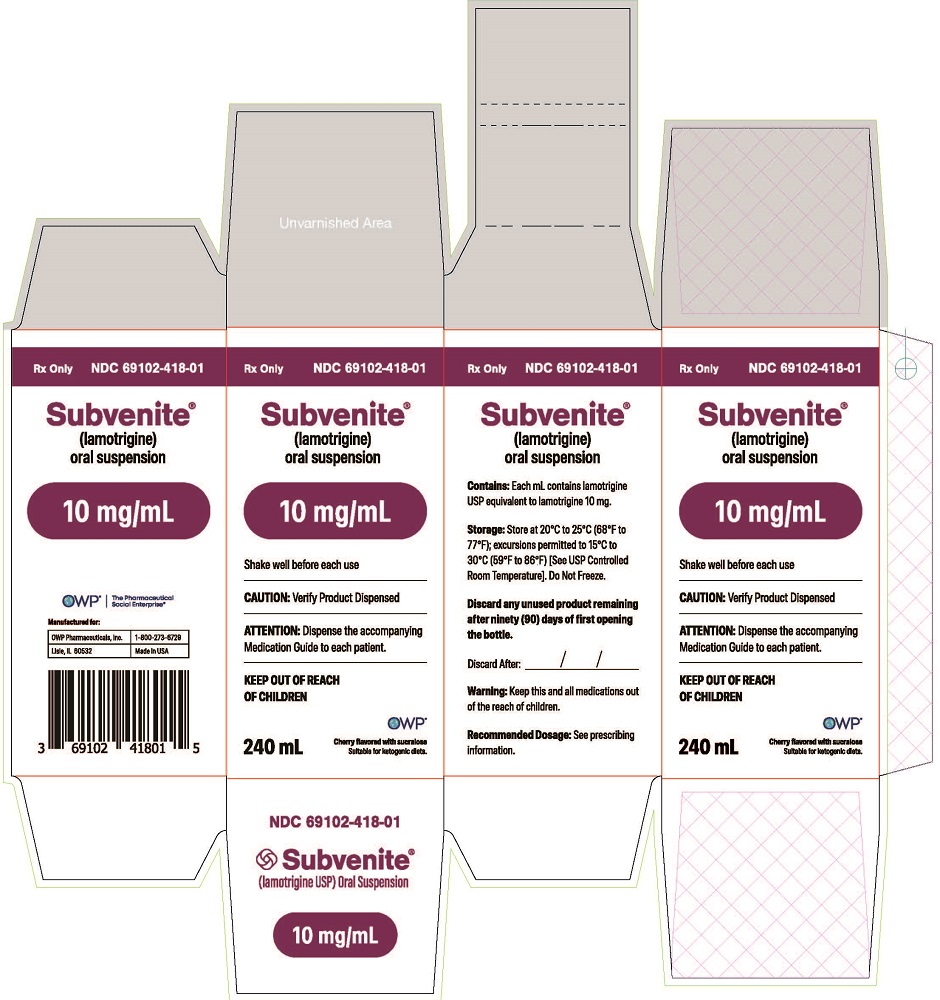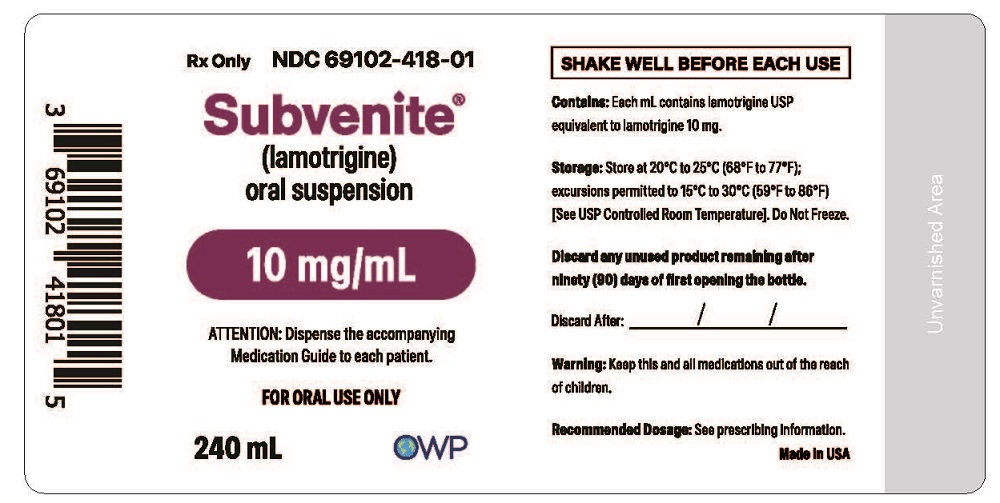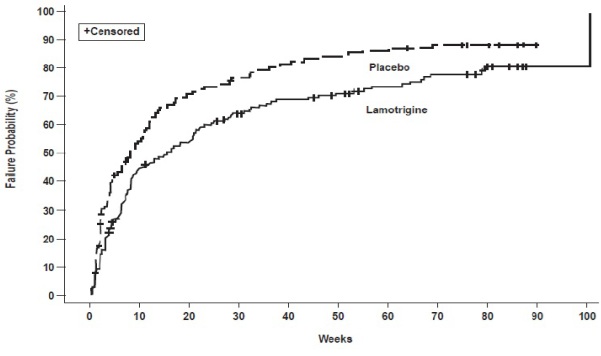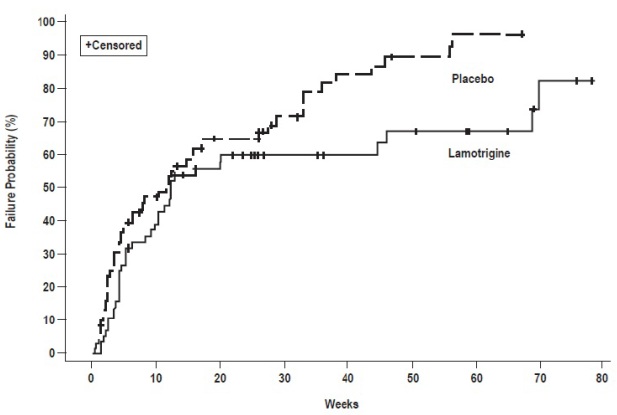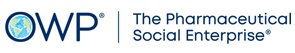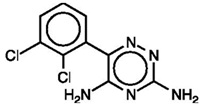 DRUG LABEL: SUBVENITE
NDC: 69102-418 | Form: SUSPENSION
Manufacturer: OWP Pharmaceuticals, Inc.
Category: prescription | Type: HUMAN PRESCRIPTION DRUG LABEL
Date: 20260116

ACTIVE INGREDIENTS: LAMOTRIGINE 10 mg/1 mL
INACTIVE INGREDIENTS: CARBOXYMETHYLCELLULOSE SODIUM; XANTHAN GUM; CELLULOSE, MICROCRYSTALLINE; SILICON DIOXIDE; SODIUM BENZOATE; SODIUM PHOSPHATE, DIBASIC; SACCHARIN SODIUM; POLYETHYLENE GLYCOL, UNSPECIFIED; METHYLPARABEN; FD&C RED NO. 40; FD&C YELLOW NO. 6; GLYCERIN; SUCRALOSE

HIGHLIGHTS OF PRESCRIBING INFORMATION

These highlights do not include all the information needed to use SUBVENITE® safely and effectively. See full prescribing information for SUBVENITE®.
SUBVENITE (lamotrigine) oral suspension
Initial U.S. Approval: 1994

BOXED WARNING

WARNING: SERIOUS SKIN RASHES

See full prescribing information for complete boxed warning.

- Cases of life-threatening serious rashes, including Stevens-Johnson syndrome and toxic epidermal necrolysis, and/or rash-related death have been caused by lamotrigine, the active ingredient in SUBVENITE. The rate of serious rash is greater in pediatric patients than in adults. Additional factors that may increase the risk of rash include:
  - coadministration with valproate.
  - exceeding recommended initial dose of SUBVENITE.
  - exceeding recommended dose escalation for SUBVENITE.
  - presence of the HLA-B*1502 allele. (5.1)
- Benign rashes are also caused by lamotrigine, the active ingredient in SUBVENITE; however, it is not possible to predict which rashes will prove to be serious or life threatening. SUBVENITE should be discontinued at the first sign of rash, unless the rash is clearly not drug related. (5.1)

1 INDICATIONS AND USAGE

SUBVENITE is indicated for:

Epilepsy—adjunctive therapy in patients aged 2 years and older:

- partial-onset seizures
- primary generalized tonic-clonic (PGTC) seizures
- generalized seizures of Lennox-Gastaut syndrome. (1.1)

Epilepsy—monotherapy in patients aged 16 years and older: Conversion to monotherapy in patients with partial-onset seizures who are receiving treatment with carbamazepine, phenytoin, phenobarbital, primidone, or valproate as the single antiepileptic drug. (1.1)

Bipolar disorder: Maintenance treatment of bipolar I disorder to delay the time to occurrence of mood episodes in patients treated for acute mood episodes with standard therapy. (1.2)

Limitations of Use: Treatment of acute manic or mixed episodes is not recommended. Effectiveness of SUBVENITE in the acute treatment of mood episodes has not been established.

2 DOSAGE AND ADMINISTRATION

- Dosing is based on concomitant medications, indication, and patient age. (2.1, 2.2, 2.3, 2.4)
- To avoid an increased risk of rash, the recommended initial dose and subsequent dose escalations should not be exceeded. (2.1, 16)
- Do not restart SUBVENITE in patients who discontinued due to rash unless the potential benefits clearly outweigh the risks. (2.1, 5.1)
- Adjustments to maintenance doses will be necessary in most patients starting or stopping estrogen-containing products, including oral contraceptives. (2.1, 5.9)
- Discontinuation: Taper over a period of at least 2 weeks (approximately 50% dose reduction per week). (2.1, 5.10)

Epilepsy:

Adjunctive therapy—See Table 1 for patients older than 12 years and Tables 2 and 3 for patients aged 2 to 12 years. (2.2)

Conversion to monotherapy—See Table 4. (2.3)

Bipolar disorder: See Tables 5 and 6. (2.4)

3 DOSAGE FORMS AND STRENGTHS

- Oral Suspension: 10 mg/mL (3)

4 CONTRAINDICATIONS

Hypersensitivity to the drug or its ingredients. (Boxed Warning, 4)

5 WARNINGS AND PRECAUTIONS

- Life-threatening serious rash and/or rash-related death: Discontinue at the first sign of rash, unless the rash is clearly not drug related. (Boxed Warning, 5.1)
- Hemophagocytic lymphohistiocytosis: Consider this diagnosis and evaluate patients immediately if they develop signs or symptoms of systemic inflammation. Discontinue lamotrigine if an alternative etiology is not established. (5.2)
- Drug Reaction with Eosinophilia and Systemic Symptoms (DRESS)/Multiorgan Hypersensitivity: Discontinue if no alternate etiology. (5.3)
- Cardiac rhythm and conduction abnormalities: Based on in vitro findings, lamotrigine could cause serious arrhythmias and/or death in patients with certain underlying cardiac disorders or arrhythmias. Any expected or observed benefit of lamotrigine in an individual patient with clinically important structural or functional heart disease must be carefully weighed against the risk for serious arrhythmias and/or death for that patient. (5.4)
- Blood dyscrasias (e.g., neutropenia, thrombocytopenia, pancytopenia): May occur, either with or without an associated hypersensitivity syndrome. Monitor for signs of anemia, unexpected infection, or bleeding. (5.5)
- Suicidal behavior and ideation: Monitor for suicidal thoughts or behaviors. (5.6)
- Aseptic meningitis: Monitor for signs of meningitis. (5.7)
- Medication errors due to product name confusion: Strongly advise patients to visually the product to verify the received drug is correct. (5.8, 16, 17)

6 ADVERSE REACTIONS

Epilepsy: Most common adverse reactions (incidence ≥10%) in adults were dizziness, headache, diplopia, ataxia, nausea, blurred vision, somnolence, rhinitis, pharyngitis, and rash. Additional adverse reactions (incidence ≥10%) reported in children included vomiting, infection, fever, accidental injury, diarrhea, abdominal pain, and tremor. (6.1)

Bipolar Disorder: Most common adverse reactions (incidence >5%) in adults were nausea, insomnia, somnolence, back pain, fatigue, rash, rhinitis, abdominal pain, and xerostomia. (6.1)

To report SUSPECTED ADVERSE REACTIONS, contact OWP Pharmaceuticals Inc. at 1-800-273-6729 or FDA at 1-800-FDA-1088 or www.fda.gov/medwatch.

7 DRUG INTERACTIONS

- Valproate increases lamot
- rigine concentrations more than 2-fold. (7, 12.3)
- Carbamazepine, phenytoin, phenobarbital, primidone, and rifampin decrease lamotrigine concentrations by approximately 40%. (7, 12.3)
- Estrogen-containing oral contraceptives decrease lamotrigine concentrations by approximately 50%. (7, 12.3)
- Protease inhibitors lopinavir/ritonavir and atazanavir/lopinavir decrease lamotrigine exposure by approximately 50% and 32%, respectively. (7, 12.3)
- Coadministration with organic cationic transporter 2 substrates with narrow therapeutic index is not recommended (7, 12.3)

8 USE IN SPECIFIC POPULATIONS

- Pregnancy: Based on animal data may cause fetal harm. (8.1)
- Hepatic impairment: Dosage adjustments required in patients with moderate and severe liver impairment. (2.1, 8.6)
- Renal impairment: Reduced maintenance doses may be effective for patients with significant renal impairment. (2.1, 8.7)

FULL PRESCRIBING INFORMATION

BOXED WARNING

WARNING: SERIOUS SKIN RASHES

SUBVENITE can cause serious rashes requiring hospitalization and discontinuation of treatment. The incidence of these rashes, which have included Stevens-Johnson syndrome, is approximately 0.3% to 0.8% in pediatric patients (aged 2 to 17 years) and 0.08% to 0.3% in adults receiving lamotrigine. One rash-related death was reported in a prospectively followed cohort of 1,983 pediatric patients (aged 2 to 16 years) with epilepsy taking lamotrigine as adjunctive therapy. In worldwide postmarketing experience, rare cases of toxic epidermal necrolysis and/or rash-related death have been reported in adult and pediatric patients, but their numbers are too few to permit a precise estimate of the rate.

In addition to age, factors that may increase the risk of occurrence or the severity of rash caused by lamotrigine include (1) coadministration of lamotrigine with valproate (includes valproic acid and divalproex sodium), (2) exceeding the recommended initial dose of lamotrigine, (3) exceeding the recommended dose escalation for lamotrigine, or (4) the presence of the HLA-B*1502 allele. However, cases have occurred in the absence of these factors.

Nearly all cases of life-threatening rashes caused by lamotrigine have occurred within 2 to 8 weeks of treatment initiation. However, isolated cases have occurred after prolonged treatment (e.g., 6 months). Accordingly, duration of therapy cannot be relied upon as means to predict the potential risk heralded by the first appearance of a rash.

Although benign rashes are also caused by lamotrigine, it is not possible to predict reliably which rashes will prove to be serious or life threatening. Accordingly, SUBVENITE should ordinarily be discontinued at the first sign of rash, unless the rash is clearly not drug related. Discontinuation of treatment may not prevent a rash from becoming life threatening or permanently disabling or disfiguring [see Warnings and Precautions (5.1)].

1 INDICATIONS AND USAGE

1.1 Epilepsy

Adjunctive Therapy

SUBVENITE is indicated as adjunctive therapy for the following seizure types in patients aged 2 years and older:

- partial-onset seizures.
- primary generalized tonic-clonic (PGTC) seizures.
- generalized seizures of Lennox-Gastaut syndrome.

Monotherapy

SUBVENITE is indicated for conversion to monotherapy in adults (aged 16 years and older) with partial-onset seizures who are receiving treatment with carbamazepine, phenytoin, phenobarbital, primidone, or valproate as the single antiepileptic drug (AED).

Safety and effectiveness of SUBVENITE have not been established (1) as initial monotherapy; (2) for conversion to monotherapy from AEDs other than carbamazepine, phenytoin, phenobarbital, primidone, or valproate; or (3) for simultaneous conversion to monotherapy from 2 or more concomitant AEDs.

1.2 Bipolar Disorder

SUBVENITE is indicated for the maintenance treatment of bipolar I disorder to delay the time to occurrence of mood episodes (depression, mania, hypomania, mixed episodes) in patients treated for acute mood episodes with standard therapy [see Clinical Studies (14.2)].

Limitations of Use

Treatment of acute manic or mixed episodes is not recommended. Effectiveness of SUBVENITE in the acute treatment of mood episodes has not been established.

2 DOSAGE AND ADMINISTRATION

2.1 General Dosing Considerations

Rash

There are suggestions that the risk of severe, potentially life-threatening rash may be increased by (1) coadministration of lamotrigine with valproate, (2) exceeding the recommended initial dose of lamotrigine, or (3) exceeding the recommended dose escalation for lamotrigine. However, cases have occurred in the absence of these factors [see Boxed Warning]. Therefore, it is important that the SUBVENITE dosing recommendations be followed closely.

The risk of nonserious rash may be increased when the recommended initial dose and/or the rate of dose escalation for SUBVENITE is exceeded and in patients with a history of allergy or rash to other AEDs.

It is recommended that SUBVENITE not be restarted in patients who discontinued due to rash associated with prior treatment with lamotrigine unless the potential benefits clearly outweigh the risks. If the decision is made to restart a patient who has discontinued lamotrigine, the need to restart with the initial dosing recommendations should be assessed. The greater the interval of time since the previous dose, the greater consideration should be given to restarting with the initial dosing recommendations. If a patient has discontinued lamotrigine for a period of more than 5 half-lives, it is recommended that initial dosing recommendations and guidelines be followed. The half-life of lamotrigine is affected by other concomitant medications [see Clinical Pharmacology (12.3)].

SUBVENITE Added to Drugs Known to Induce or Inhibit Glucuronidation

Because lamotrigine is metabolized predominantly by glucuronic acid conjugation, drugs that are known to induce or inhibit glucuronidation may affect the apparent clearance of lamotrigine. Drugs that induce glucuronidation include carbamazepine, phenytoin, phenobarbital, primidone, rifampin, estrogen-containing products, including oral contraceptives, and the protease inhibitors lopinavir/ritonavir and atazanavir/ritonavir. Valproate inhibits glucuronidation. For dosing considerations for SUBVENITE in patients on estrogen-containing products, including contraceptives, and atazanavir/ritonavir, see below and Table 13. For dosing considerations for SUBVENITE in patients on other drugs known to induce or inhibit glucuronidation, see Tables 1, 2, 5 to 6, and 13.

Target Plasma Levels for Patients with Epilepsy or Bipolar Disorder

A therapeutic plasma concentration range has not been established for lamotrigine. Dosing of SUBVENITE should be based on therapeutic response [see Clinical Pharmacology (12.3)].

Women Taking Estrogen-Containing Oral Contraceptives

Starting SUBVENITE in Women Taking Estrogen-Containing Oral Contraceptives: Although estrogen-containing oral contraceptives have been shown to increase the clearance of lamotrigine, no adjustments to the recommended dose-escalation guidelines for SUBVENITE should be necessary solely based on the use of estrogen-containing oral contraceptives [see Clinical Pharmacology (12.3)]. Therefore, dose escalation should follow the recommended guidelines for initiating adjunctive therapy with SUBVENITE based on the concomitant AED or other concomitant medications (see Tables 1, 5, and 7). See below for adjustments to maintenance doses of SUBVENITE in women taking estrogen-containing oral contraceptives.

Adjustments to the Maintenance Dose of SUBVENITE in Women Taking Estrogen-Containing Oral Contraceptives:

(1) Taking Estrogen-Containing Oral Contraceptives: In women not taking carbamazepine, phenytoin, phenobarbital, primidone, or other drugs such as rifampin and the protease inhibitors lopinavir/ritonavir and atazanavir/ritonavir that induce lamotrigine glucuronidation, the maintenance dose of SUBVENITE will in most cases need to be increased by as much as 2-fold over the recommended target maintenance dose to maintain a consistent lamotrigine plasma level [see Drug Interactions (7), Clinical Pharmacology (12.3)].

(2) Starting Estrogen-Containing Oral Contraceptives: In women taking a stable dose of SUBVENITE and not taking carbamazepine, phenytoin, phenobarbital, primidone, or other drugs such as rifampin and the protease inhibitors lopinavir/ritonavir and atazanavir/ritonavir that induce lamotrigine glucuronidation, the maintenance dose will in most cases need to be increased by as much as 2-fold to maintain a consistent lamotrigine plasma level [see Drug Interactions (7), Clinical Pharmacology (12.3)]. The dose increases should begin at the same time that the oral contraceptive is introduced and continue, based on clinical response, no more rapidly than 50 to 100 mg/day every week. Dose increases should not exceed the recommended rate (see Tables 1 and 5) unless lamotrigine plasma levels or clinical response support larger increases. Gradual transient increases in lamotrigine plasma levels may occur during the week of inactive hormonal preparation (pill-free week), and these increases will be greater if dose increases are made in the days before or during the week of inactive hormonal preparation. Increased lamotrigine plasma levels could result in additional adverse reactions, such as dizziness, ataxia, and diplopia. If adverse reactions attributable to SUBVENITE consistently occur during the pill-free week, dose adjustments to the overall maintenance dose may be necessary. Dose adjustments limited to the pill-free week are not recommended. For women taking SUBVENITE in addition to carbamazepine, phenytoin, phenobarbital, primidone, or other drugs such as rifampin and the protease inhibitors lopinavir/ritonavir and atazanavir/ritonavir that induce lamotrigine glucuronidation, no adjustment to the dose of SUBVENITE should be necessary [see Drug Interactions (7), Clinical Pharmacology (12.3)].

(3) Stopping Estrogen-Containing Oral Contraceptives: In women not taking carbamazepine, phenytoin, phenobarbital, primidone, or other drugs such as rifampin and the protease inhibitors lopinavir/ritonavir and atazanavir/ritonavir that induce lamotrigine glucuronidation, the maintenance dose of SUBVENITE will in most cases need to be decreased by as much as 50% in order to maintain a consistent lamotrigine plasma level [see Drug Interactions (7), Clinical Pharmacology (12.3)]. The decrease in dose of SUBVENITE should not exceed 25% of the total daily dose per week over a 2-week period, unless clinical response or lamotrigine plasma levels indicate otherwise [see Clinical Pharmacology (12.3)]. In women taking SUBVENITE in addition to carbamazepine, phenytoin, phenobarbital, primidone, or other drugs such as rifampin and the protease inhibitors lopinavir/ritonavir and atazanavir/ritonavir that induce lamotrigine glucuronidation, no adjustment to the dose of SUBVENITE should be necessary [see Drug Interactions (7), Clinical Pharmacology (12.3)].

Women and Other Hormonal Contraceptive Preparations or Hormone Replacement Therapy

The effect of other hormonal contraceptive preparations or hormone replacement therapy (HRT) on the pharmacokinetics of lamotrigine has not been systematically evaluated. Other estrogen‑containing therapies, such as HRT, may interfere with lamotrigine. Therefore, close clinical monitoring on effectiveness of SUBVENITE with dose adjustment may be necessary [see Warnings and Precautions (5.9)]. It has been reported that ethinylestradiol, not progestogens, increased the clearance of lamotrigine up to 2-fold, and the progestin-only pills had no effect on lamotrigine plasma levels. Therefore, adjustments to the dosage of SUBVENITE in the presence of progestogens alone will likely not be needed.

Patients Taking Atazanavir/Ritonavir

While atazanavir/ritonavir does reduce the lamotrigine plasma concentration, no adjustments to the recommended dose-escalation guidelines for SUBVENITE should be necessary solely based on the use of atazanavir/ritonavir. Dose escalation should follow the recommended guidelines for initiating adjunctive therapy with SUBVENITE based on concomitant AED or other concomitant medications (see Tables 1, 2, and 5). In patients already taking maintenance doses of SUBVENITE and not taking glucuronidation inducers, the dose of SUBVENITE may need to be increased if atazanavir/ritonavir is added, or decreased if atazanavir/ritonavir is discontinued [see Clinical Pharmacology (12.3)].

Patients with Hepatic Impairment

Experience in patients with hepatic impairment is limited. Based on a clinical pharmacology study in 24 subjects with mild, moderate, and severe liver impairment, the following general recommendations can be made [see Use in Specific Populations (8.6), Clinical Pharmacology (12.3)]. No dosage adjustment is needed in patients with mild liver impairment. Initial, escalation, and maintenance doses should generally be reduced by approximately 25% in patients with moderate and severe liver impairment without ascites and 50% in patients with severe liver impairment with ascites. Escalation and maintenance doses may be adjusted according to clinical response.

Patients with Renal Impairment

Initial doses of SUBVENITE should be based on patients' concomitant medications (see Tables 1 to 3, and 5); reduced maintenance doses may be effective for patients with significant renal impairment [see Use in Specific Populations (8.7), Clinical Pharmacology (12.3)]. Few patients with severe renal impairment have been evaluated during chronic treatment with lamotrigine. Because there is inadequate experience in this population, SUBVENITE should be used with caution in these patients.

Discontinuation Strategy

Epilepsy: For patients receiving SUBVENITE in combination with other AEDs, a re-evaluation of all AEDs in the regimen should be considered if a change in seizure control or an appearance or worsening of adverse reactions is observed.

If a decision is made to discontinue therapy with SUBVENITE, a step-wise reduction of dose over at least 2 weeks (approximately 50% per week) is recommended unless safety concerns require a more rapid withdrawal [see Warnings and Precautions (5.10)].

Discontinuing carbamazepine, phenytoin, phenobarbital, primidone, or other drugs such as rifampin and the protease inhibitors lopinavir/ritonavir and atazanavir/ritonavir that induce lamotrigine glucuronidation should prolong the half-life of lamotrigine; discontinuing valproate should shorten the half-life of lamotrigine.

Bipolar Disorder: In the controlled clinical trials, there was no increase in the incidence, type, or severity of adverse reactions following abrupt termination of lamotrigine. In the clinical development program in adults with bipolar disorder, 2 patients experienced seizures shortly after abrupt withdrawal of lamotrigine. Discontinuation of SUBVENITE should involve a step-wise reduction of dose over at least 2 weeks (approximately 50% per week) unless safety concerns require a more rapid withdrawal [see Warnings and Precautions (5.10)].

2.2 Epilepsy—Adjunctive Therapy

This section provides specific dosing recommendations for patients older than 12 years and patients aged 2 to 12 years. Within each of these age-groups, specific dosing recommendations are provided depending upon concomitant AEDs or other concomitant medications (see Table 1 for patients older than 12 years and Table 2 for patients aged 2 to 12 years).

Patients Older than 12 Years

Recommended dosing guidelines are summarized in Table 1.

Table 1. Escalation Regimen for SUBVENITE in Patients Older than 12 Years with Epilepsy
 | In Patients TAKING Valproatea | In Patients NOT TAKING Carbamazepine, Phenytoin, Phenobarbital, Primidoneb, or Valproatea | In Patients TAKING Carbamazepine, Phenytoin, Phenobarbital, or Primidoneb and NOT TAKING Valproatea
Weeks 1 and 2 | 25 mg every other day | 25 mg every day | 50 mg/day
Weeks 3 and 4 | 25 mg every day | 50 mg/day | 100 mg/day (in 2 divided doses)
Week 5 onward to maintenance | Increase by 25 to 50 mg/day every 1 to 2 weeks. | Increase by 50 mg/day every 1 to 2 weeks. | Increase by 100 mg/day every 1 to 2 weeks.
Usual maintenance dose | 100 to 200 mg/day with valproate alone 100 to 400 mg/day with valproate and other drugs that induce glucuronidation (in 1 or 2 divided doses) | 225 to 375 mg/day (in 2 divided doses) | 300 to 500 mg/day (in 2 divided doses)
a Valproate has been shown to inhibit glucuronidation and decrease the apparent clearance of lamotrigine [see Drug Interactions (7), Clinical Pharmacology (12.3)].
b Drugs that induce lamotrigine glucuronidation and increase clearance, other than the specified AEDs, include estrogen-containing oral contraceptives, rifampin, and the protease inhibitors lopinavir/ritonavir and atazanavir/ritonavir. Dosing recommendations for estrogen-containing products, including oral contraceptives, and the protease inhibitor atazanavir/ritonavir can be found in General Dosing Considerations [see Dosage and Administration (2.1)]. Patients on rifampin and the protease inhibitor lopinavir/ritonavir should follow the same dosing titration/maintenance regimen used with antiepileptic drugs that induce glucuronidation and increase clearance [see Dosage and Administration (2.1), Drug Interactions (7), Clinical Pharmacology (12.3)].

Patients Aged 2 to 12 Years

Recommended dosing guidelines are summarized in Table 2.

Lower starting doses and slower dose escalations than those used in clinical trials are recommended because of the suggestion that the risk of rash may be decreased by lower starting doses and slower dose escalations. Therefore, maintenance doses will take longer to reach in clinical practice than in clinical trials. It may take several weeks to months to achieve an individualized maintenance dose. Maintenance doses in patients weighing <30 kg, regardless of age or concomitant AED, may need to be increased as much as 50%, based on clinical response.

Table 2. Escalation Regimen for SUBVENITE in Patients Aged 2 to 12 Years with Epilepsy
 | In Patients TAKING Valproatea | In Patients NOT TAKING Carbamazepine, Phenytoin, Phenobarbital, Primidoneb, or Valproatea | In Patients TAKING Carbamazepine, Phenytoin, Phenobarbital, or Primidoneb and NOT TAKING Valproatea
Weeks 1 and 2 | 0.15 mg/kg/day in 1 or 2 divided doses | 0.3 mg/kg/day in 1 or 2 divided doses | 0.6 mg/kg/day in 2 divided doses
Weeks 3 and 4 | 0.3 mg/kg/day in 1 or 2 divided doses | 0.6 mg/kg/day in 2 divided doses | 1.2 mg/kg/day in 2 divided doses
Week 5 onward to maintenance | The dose should be increased every 1 to 2 weeks as follows: calculate 0.3 mg/kg/day, add this amount to the previously administered daily dose. | The dose should be increased every 1 to 2 weeks as follows: calculate 0.6 mg/kg/day, add this amount to the previously administered daily dose. | The dose should be increased every 1 to 2 weeks as follows: calculate 1.2 mg/kg/day, add this amount to the previously administered daily dose.
Usual maintenance dose | 1 to 5 mg/kg/day (maximum 200 mg/day in 1 or 2 divided doses) 1 to 3 mg/kg/day with valproate alone | 4.5 to 7.5 mg/kg/day (maximum 300 mg/day in 2 divided doses) | 5 to 15 mg/kg/day (maximum 400 mg/day in 2 divided doses)
Maintenance dose in patients <30 kg | May need to be increased by as much as 50%, based on clinical response. | May need to be increased by as much as 50%, based on clinical response. | May need to be increased by as much as 50%, based on clinical response.
a Valproate has been shown to inhibit glucuronidation and decrease the apparent clearance of lamotrigine [see Drug Interactions (7), Clinical Pharmacology (12.3)].
b Drugs that induce lamotrigine glucuronidation and increase clearance, other than the specified AEDs, include estrogen-containing oral contraceptives, rifampin, and the protease inhibitors lopinavir/ritonavir and atazanavir/ritonavir. Dosing recommendations for estrogen-containing products, including oral contraceptives, and the protease inhibitor atazanavir/ritonavir, can be found in General Dosing Considerations [see Dosage and Administration (2.1)]. Patients on rifampin and the protease inhibitor lopinavir/ritonavir should follow the same dosing titration/maintenance regimen used with AEDs that induce glucuronidation and increase clearance [see Dosage and Administration (2.1), Drug Interactions (7), Clinical Pharmacology (12.3)].

Usual Adjunctive Maintenance Dose for Epilepsy

The usual maintenance doses identified in Tables 1 and 2 are derived from dosing regimens employed in the placebo-controlled adjunctive trials in which the efficacy of lamotrigine was established. In patients receiving multidrug regimens employing carbamazepine, phenytoin, phenobarbital, or primidone without valproate, maintenance doses of adjunctive lamotrigine as high as 700 mg/day have been used. In patients receiving valproate alone, maintenance doses of adjunctive lamotrigine as high as 200 mg/day have been used. The advantage of using doses above those recommended in Tables 1 to 3 has not been established in controlled trials.

2.3 Epilepsy-Conversion from Adjunctive Therapy to Monotherapy

The goal of the transition regimen is to attempt to maintain seizure control while mitigating the risk of serious rash associated with the rapid titration of lamotrigine.

The recommended maintenance dose of SUBVENITE as monotherapy is 500 mg/day given in 2 divided doses.

To avoid an increased risk of rash, the recommended initial dose and subsequent dose escalations for SUBVENITE should not be exceeded [see Boxed Warning].

Conversion from Adjunctive Therapy with Carbamazepine, Phenytoin, Phenobarbital, or Primidone to Monotherapy with SUBVENITE

After achieving a dose of 500 mg/day of SUBVENITE using the guidelines in Table 1, the concomitant enzyme-inducing AED should be withdrawn by 20% decrements each week over a 4-week period. The regimen for the withdrawal of the concomitant AED is based on experience gained in the controlled monotherapy clinical trial.

Conversion from Adjunctive Therapy with Valproate to Monotherapy with SUBVENITE

The conversion regimen involves the 4 steps outlined in Table 3.

Table 3. Conversion from Adjunctive Therapy with Valproate to Monotherapy with SUBVENITE in Patients Aged 16 Years and Older with Epilepsy
 | SUBVENITE | Valproate
Step 1 | Achieve a dose of 200 mg/day according to guidelines in Table 1. | Maintain established stable dose.
Step 2 | Maintain at 200 mg/day. | Decrease dose by decrements no greater than 500 mg/day/week to 500 mg/day and then maintain for 1 week.
Step 3 | Increase to 300 mg/day and maintain for 1 week. | Simultaneously decrease to 250 mg/day and maintain for 1 week.
Step 4 | Increase by 100 mg/day every week to achieve maintenance dose of 500 mg/day. | Discontinue.

Conversion from Adjunctive Therapy with Antiepileptic Drugs other than Carbamazepine, Phenytoin, Phenobarbital, Primidone, or Valproate to Monotherapy with SUBVENITE

No specific dosing guidelines can be provided for conversion to monotherapy with SUBVENITE with AEDs other than carbamazepine, phenytoin, phenobarbital, primidone, or valproate.

2.4 Bipolar Disorder

The goal of maintenance treatment with SUBVENITE is to delay the time to occurrence of mood episodes (depression, mania, hypomania, mixed episodes) in patients treated for acute mood episodes with standard therapy [see Indications and Usage (1.2)].

Patients taking lamotrigine for more than 16 weeks should be periodically reassessed to determine the need for maintenance treatment.

Adults

The target dose of SUBVENITE is 200 mg/day (100 mg/day in patients taking valproate, which decreases the apparent clearance of lamotrigine, and 400 mg/day in patients not taking valproate and taking either carbamazepine, phenytoin, phenobarbital, primidone, or other drugs such as rifampin and the protease inhibitor lopinavir/ritonavir that increase the apparent clearance of lamotrigine). In the clinical trials, doses up to 400 mg/day as monotherapy were evaluated; however, no additional benefit was seen at 400 mg/day compared with 200 mg/day [see Clinical Studies (14.2)]. Accordingly, doses above 200 mg/day are not recommended.

Treatment with SUBVENITE is introduced, based on concurrent medications, according to the regimen outlined in Table 4. If other psychotropic medications are withdrawn following stabilization, the dose of SUBVENITE should be adjusted. In patients discontinuing valproate, the dose of SUBVENITE should be doubled over a 2-week period in equal weekly increments (see Table 5). In patients discontinuing carbamazepine, phenytoin, phenobarbital, primidone, or other drugs such as rifampin and the protease inhibitors lopinavir/ritonavir and atazanavir/ritonavir that induce lamotrigine glucuronidation, the dose of SUBVENITE should remain constant for the first week and then should be decreased by half over a 2-week period in equal weekly decrements (see Table 5). The dose of SUBVENITE may then be further adjusted to the target dose (200 mg) as clinically indicated.

If other drugs are subsequently introduced, the dose of SUBVENITE may need to be adjusted. In particular, the introduction of valproate requires reduction in the dose of SUBVENITE [see Drug Interactions (7), Clinical Pharmacology (12.3)].

To avoid an increased risk of rash, the recommended initial dose and subsequent dose escalations of SUBVENITE should not be exceeded [see Boxed Warning].

Table 4. Escalation Regimen for SUBVENITE in Adults with Bipolar Disorder
 | In Patients TAKING Valproatea | In Patients NOT TAKING Carbamazepine, Phenytoin, Phenobarbital, Primidoneb, or Valproatea | In Patients TAKING Carbamazepine, Phenytoin, Phenobarbital, or Primidoneb and NOT TAKING Valproatea
Weeks 1 and 2 | 25 mg every other day | 25 mg daily | 50 mg daily
Weeks 3 and 4 | 25 mg daily | 50 mg daily | 100 mg daily, in divided doses
Week 5 | 50 mg daily | 100 mg daily | 200 mg daily, in divided doses
Week 6 | 100 mg daily | 200 mg daily | 300 mg daily, in divided doses
Week 7 | 100 mg daily | 200 mg daily | up to 400 mg daily, in divided doses
a Valproate has been shown to inhibit glucuronidation and decrease the apparent clearance of lamotrigine [see Drug Interactions (7), Clinical Pharmacology (12.3)].
b Drugs that induce lamotrigine glucuronidation and increase clearance, other than the specified AEDs, include estrogen-containing products, including oral contraceptives, rifampin, and the protease inhibitors lopinavir/ritonavir and atazanavir/ritonavir. Dosing recommendations for oral contraceptives and the protease inhibitor atazanavir/ritonavir can be found in General Dosing Considerations [see Dosage and Administration (2.1)]. Patients on rifampin and the protease inhibitor lopinavir/ritonavir should follow the same dosing titration/maintenance regimen used with AEDs that induce glucuronidation and increase clearance [see Dosage and Administration (2.1), Drug Interactions (7), Clinical Pharmacology (12.3)].

Table 5. Dosage Adjustments to lamotrigine in Adults with Bipolar Disorder Following Discontinuation of Psychotropic Medications
 | Discontinuation of Psychotropic Drugs (excluding Valproatea, Carbamazepine, Phenytoin, Phenobarbital, or Primidoneb) | After Discontinuation of Valproatea | After Discontinuation of Carbamazepine, Phenytoin, Phenobarbital, or Primidoneb
 | Discontinuation of Psychotropic Drugs (excluding Valproatea, Carbamazepine, Phenytoin, Phenobarbital, or Primidoneb) | Current Dose of SUBVENITE 100 mg/day | Current Dose of SUBVENITE 400 mg/day
Week 1 | Maintain current dose of SUBVENITE | 150 mg/day | 400 mg/day
Week 2 | Maintain current dose of SUBVENITE | 200 mg/day | 300 mg/day
Week 3 onward | Maintain current dose of SUBVENITE | 200 mg/day | 200 mg/day
a Valproate has been shown to inhibit glucuronidation and decrease the apparent clearance of lamotrigine [see Drug Interactions (7), Clinical Pharmacology (12.3)].
b Drugs that induce lamotrigine glucuronidation and increase clearance, other than the specified AEDs, include estrogen-containing products, including oral contraceptives, rifampin, and the protease inhibitors lopinavir/ritonavir and atazanavir/ritonavir. Dosing recommendations for oral contraceptives and the protease inhibitor atazanavir/ritonavir can be found in General Dosing Considerations [see Dosage and Administration (2.1)]. Patients on rifampin and the protease inhibitor lopinavir/ritonavir should follow the same dosing titration/maintenance regimen used with AEDs that induce glucuronidation and increase clearance [see Dosage and Administration (2.1), Drug Interactions (7), Clinical Pharmacology (12.3)].

2.5 Administration Instructions

SUBVENITE can be administered with or without food.

Use a calibrated measuring device, such as an oral dosing syringe or oral dosing cup, to measure and deliver the prescribed dose accurately. A household teaspoon or tablespoon is not an adequate measuring device.

Shake well before each use. Discard any unused portion 90 days after first opening.

3 DOSAGE FORMS AND STRENGTHS

SUBVENITE oral suspension 10 mg/mL is supplied as a pink, cherry-flavored liquid.

4 CONTRAINDICATIONS

SUBVENITE is contraindicated in patients who have demonstrated hypersensitivity (e.g., rash, angioedema, acute urticaria, extensive pruritus, mucosal ulceration) to the drug or its ingredients [see Boxed Warning, Warnings and Precautions (5.1, 5.3)].

5 WARNINGS AND PRECAUTIONS

5.1 Serious Skin Rashes [see Boxed Warning]

Pediatric Population

The incidence of serious rash associated with hospitalization and discontinuation of lamotrigine in a prospectively followed cohort of pediatric patients (aged 2 to 17 years) is approximately 0.3% to 0.8%. One rash-related death was reported in a prospectively followed cohort of 1,983 pediatric patients (aged 2 to 16 years) with epilepsy taking lamotrigine as adjunctive therapy. Additionally, there have been rare cases of toxic epidermal necrolysis (TEN) with and without permanent sequelae and/or death in U.S. and foreign postmarketing experience.

There is evidence that the inclusion of valproate in a multidrug regimen increases the risk of serious, potentially life-threatening rash in pediatric patients. In pediatric patients who used valproate concomitantly for epilepsy, 1.2% (6 of 482) experienced a serious rash compared with 0.6% (6 of 952) patients not taking valproate.

Adult Population

Serious rash associated with hospitalization and discontinuation of lamotrigine occurred in 0.3% (11 of 3,348) of adult patients who received lamotrigine in premarketing clinical trials of epilepsy. In the bipolar and other mood disorders clinical trials, the rate of serious rash was 0.08% (1 of 1,233) of adult patients who received lamotrigine as initial monotherapy and 0.13% (2 of 1,538) of adult patients who received lamotrigine as adjunctive therapy. No fatalities occurred among these individuals. However, in worldwide postmarketing experience, rare cases of rash-related death have been reported, but their numbers are too few to permit a precise estimate of the rate.

Among the rashes leading to hospitalization were Stevens-Johnson syndrome, toxic epidermal necrolysis, angioedema, and those associated with multiorgan hypersensitivity [see Warnings and Precautions (5.3)].

Risk Factors

Concomitant Use of Valproate

There is evidence that the inclusion of valproate in a multidrug regimen increases the risk of serious, potentially life-threatening rash in adults. Specifically, of 584 patients administered lamotrigine with valproate in epilepsy clinical trials, 6 (1%) were hospitalized in association with rash; in contrast, 4 (0.16%) of 2,398 clinical trial patients and volunteers administered lamotrigine in the absence of valproate were hospitalized.

Patients with History of Allergy or Rash to Other Antiepileptic Drugs

The risk of rash may be increased in patients with a history of allergy or rash to other AEDs.

Not Adhering to the Recommended Dosage

The risk of rash is increased by both exceeding the recommended initial dose of SUBVENITE and exceeding the recommended dose escalation for SUBVENITE.

Patients with Genetic Variant Human Leukocyte Antigen (HLA)-B*1502 Allele

Retrospective case-control studies in patients of certain Asian ancestry (e.g., Han Chinese and Thai) suggest that the HLA-B*1502 allele is associated with an increased risk (approximately 2-3 times higher) of developing Stevens-Johnson syndrome (SJS)/toxic epidermal necrolysis (TEN) in patients using lamotrigine. The risks and benefits of therapy should be weighed when considering use of SUBVENITE in patients known to be positive for HLA-B*1502. Application of HLA genotyping as a screening tool has important limitations and must never substitute for appropriate clinical vigilance and patient management. Many HLA B*1502 positive patients treated with SUBVENITE will not develop SJS/TEN or other hypersensitivity reactions, and these reactions can still occur in HLA B*1502 negative patients of any ethnicity.

5.2 Hemophagocytic Lymphohistiocytosis

Hemophagocytic lymphohistiocytosis (HLH) has occurred in pediatric and adult patients taking lamotrigine, the active ingredient in SUBVENITE, for various indications. HLH is a life-threatening syndrome of pathologic immune activation characterized by clinical signs and symptoms of extreme systemic inflammation. It is associated with high mortality rates if not recognized early and treated. Common findings include fever, hepatosplenomegaly, rash, lymphadenopathy, neurologic symptoms, cytopenias, high serum ferritin, hypertriglyceridemia, and liver function and coagulation abnormalities. In cases of HLH reported with lamotrigine, patients have presented with signs of systemic inflammation (fever, rash, hepatosplenomegaly, and organ system dysfunction) and blood dyscrasias. Symptoms have been reported to occur within 8 to 24 days following the initiation of treatment. Patients who develop early manifestations of pathologic immune activation should be evaluated immediately, and a diagnosis of HLH should be considered. SUBVENITE should be discontinued if an alternative etiology for the signs or symptoms cannot be established.

5.3 Drug Reaction with Eosinophilia and Systemic Symptoms (DRESS)/Multiorgan Hypersensitivity

Drug Reaction with Eosinophilia and Systemic Symptoms (DRESS), also known as multiorgan hypersensitivity, has occurred with patients taking antiepileptic drugs, including lamotrigine, the active ingredient in SUBVENITE. These events can be fatal or life threatening, particularly if diagnosis and treatment do not occur as early as possible. DRESS typically, although not exclusively, presents with fever, rash, lymphadenopathy, and/or facial swelling, in association with other organ system involvement, such as hepatitis, nephritis, hematologic abnormalities, myocarditis, or myositis, sometimes resembling an acute viral infection. Eosinophilia is often present. Because this disorder is variable in its expression, other organ systems not noted here may be involved.

Fatalities associated with acute multiorgan failure and various degrees of hepatic failure have been reported in 2 of 3,796 adult patients and 4 of 2,435 pediatric patients who received lamotrigine in epilepsy clinical trials. Rare fatalities from multiorgan failure have also been reported in postmarketing use.

Isolated liver failure without rash or involvement of other organs has also been reported with lamotrigine.

It is important to note that early manifestations of hypersensitivity (e.g., fever, lymphadenopathy) may be present even though a rash is not evident. If such signs or symptoms are present, the patient should be evaluated immediately. SUBVENITE should be discontinued if an alternative etiology for the signs or symptoms cannot be established.

5.4 Cardiac Rhythm and Conduction Abnormalities

In vitro testing showed that lamotrigine exhibits Class IB antiarrhythmic activity at therapeutically relevant concentrations [see Clinical Pharmacology (12.2)]. Based on these in vitro findings, SUBVENITE could slow ventricular conduction (widen QRS) and induce proarrhythmia, which can lead to sudden death, in patients with clinically important structural or functional heart disease (i.e., patients with heart failure, valvular heart disease, congenital heart disease, conduction system disease, ventricular arrhythmias, cardiac channelopathies [e.g., Brugada syndrome], clinically important ischemic heart disease, or multiple risk factors for coronary artery disease). Elevated heart rates could also increase the risk of ventricular conduction slowing with SUBVENITE. Any expected or observed benefit of SUBVENITE in an individual patient with clinically important structural or functional heart disease must be carefully weighed against the risks for serious arrhythmias and/or death for that patient. Concomitant use of other sodium channel blockers may further increase the risk of proarrhythmia.

5.5 Blood Dyscrasias

There have been reports of blood dyscrasias that may or may not be associated with multiorgan hypersensitivity (also known as DRESS) [see Warnings and Precautions (5.3)]. These have included neutropenia, leukopenia, anemia, thrombocytopenia, pancytopenia, and, rarely, aplastic anemia and pure red cell aplasia.

5.6 Suicidal Behavior and Ideation

AEDs, including SUBVENITE, increase the risk of suicidal thoughts or behavior in patients taking these drugs for any indication. Patients treated with any AED for any indication should be monitored for the emergence or worsening of depression, suicidal thoughts or behavior, and/or any unusual changes in mood or behavior.

Pooled analyses of 199 placebo-controlled clinical trials (monotherapy and adjunctive therapy) of 11 different AEDs showed that patients randomized to 1 of the AEDs had approximately twice the risk (adjusted Relative Risk 1.8, 95% CI: 1.2, 2.7) of suicidal thinking or behavior compared with patients randomized to placebo. In these trials, which had a median treatment duration of 12 weeks, the estimated incidence of suicidal behavior or ideation among 27,863 AED-treated patients was 0.43%, compared with 0.24% among 16,029 placebo-treated patients, representing an increase of approximately 1 case of suicidal thinking or behavior for every 530 patients treated. There were 4 suicides in drug-treated patients in the trials and none in placebo-treated patients, but the number of events is too small to allow any conclusion about drug effect on suicide.

The increased risk of suicidal thoughts or behavior with AEDs was observed as early as 1 week after starting treatment with AEDs and persisted for the duration of treatment assessed. Because most trials included in the analysis did not extend beyond 24 weeks, the risk of suicidal thoughts or behavior beyond 24 weeks could not be assessed.

The risk of suicidal thoughts or behavior was generally consistent among drugs in the data analyzed. The finding of increased risk with AEDs of varying mechanism of action and across a range of indications suggests that the risk applies to all AEDs used for any indication. The risk did not vary substantially by age (5 to 100 years) in the clinical trials analyzed.

Table 6 shows absolute and relative risk by indication for all evaluated AEDs.

Table 6. Risk by Indication for Antiepileptic Drugs in the Pooled Analysis
Indication | Placebo Patients with Events per 1,000 Patients | Drug Patients with Events per 1,000 Patients | Relative Risk: Incidence of Events in Drug Patients/Incidence in Placebo Patients | Risk Difference: Additional Drug Patients with Events per 1,000 Patients
Epilepsy | 1.0 | 3.4 | 3.5 | 2.4
Psychiatric | 5.7 | 8.5 | 1.5 | 2.9
Other | 1.0 | 1.8 | 1.9 | 0.9
Total | 2.4 | 4.3 | 1.8 | 1.9

The relative risk for suicidal thoughts or behavior was higher in clinical trials for epilepsy than in clinical trials for psychiatric or other conditions, but the absolute risk differences were similar for the epilepsy and psychiatric indications.

Anyone considering prescribing SUBVENITE or any other AED must balance the risk of suicidal thoughts or behavior with the risk of untreated illness. Epilepsy and many other illnesses for which AEDs are prescribed are themselves associated with morbidity and mortality and an increased risk of suicidal thoughts and behavior. Should suicidal thoughts and behavior emerge during treatment, the prescriber needs to consider whether the emergence of these symptoms in any given patient may be related to the illness being treated.

Patients, their caregivers, and families should be informed that AEDs increase the risk of suicidal thoughts and behavior and should be advised of the need to be alert for the emergence or worsening of the signs and symptoms of depression, any unusual changes in mood or behavior, the emergence of suicidal thoughts or suicidal behavior, or thoughts about self-harm. Behaviors of concern should be reported immediately to healthcare providers.

5.7 Aseptic Meningitis

Therapy with SUBVENITE increases the risk of developing aseptic meningitis. Because of the potential for serious outcomes of untreated meningitis due to other causes, patients should also be evaluated for other causes of meningitis and treated as appropriate.

Postmarketing cases of aseptic meningitis have been reported in pediatric and adult patients taking lamotrigine for various indications. Symptoms upon presentation have included headache, fever, nausea, vomiting, and nuchal rigidity. Rash, photophobia, myalgia, chills, altered consciousness, and somnolence were also noted in some cases. Symptoms have been reported to occur within 1 day to one and a half months following the initiation of treatment. In most cases, symptoms were reported to resolve after discontinuation of lamotrigine. Re-exposure resulted in a rapid return of symptoms (from within 30 minutes to 1 day following re-initiation of treatment) that were frequently more severe. Some of the patients treated with SUBVENITE who developed aseptic meningitis had underlying diagnoses of systemic lupus erythematosus or other autoimmune diseases.

Cerebrospinal fluid (CSF) analyzed at the time of clinical presentation in reported cases was characterized by a mild to moderate pleocytosis, normal glucose levels, and mild to moderate increase in protein. CSF white blood cell count differentials showed a predominance of neutrophils in a majority of the cases, although a predominance of lymphocytes was reported in approximately one third of the cases. Some patients also had new onset of signs and symptoms of involvement of other organs (predominantly hepatic and renal involvement), which may suggest that in these cases the aseptic meningitis observed was part of a hypersensitivity reaction [see Warnings and Precautions (5.3)].

5.8 Potential Medication Errors

Medication errors involving lamotrigine have occurred. In particular, the name lamotrigine can be confused with the names of other commonly used medications. Medication errors may also occur between the different formulations of lamotrigine. To reduce the potential for medication errors, write and say SUBVENITE clearly. SUBVENITE is a pink oral suspension. To avoid the medication error of using the wrong drug or formulation, patients should be strongly advised to visually inspect the product to verify that it is SUBVENITE oral suspension, each time they fill their prescription.

5.9 Concomitant Use with Estrogen-Containing Products, Including Oral Contraceptives

Some estrogen-containing oral contraceptives have been shown to decrease serum concentrations of lamotrigine [see Clinical Pharmacology (12.3)]. Dosage adjustments will be necessary in most patients who start or stop estrogen-containing oral contraceptives while taking SUBVENITE [see Dosage and Administration (2.1)]. During the week of inactive hormone preparation (pill-free week) of oral contraceptive therapy, plasma lamotrigine levels are expected to rise, as much as doubling at the end of the week. Adverse reactions consistent with elevated levels of lamotrigine, such as dizziness, ataxia, and diplopia, could occur. Other oral contraceptive and other estrogen-containing therapies (such as HRT) have not been studied, though they may similarly affect lamotrigine pharmacokinetic parameters.

5.10 Withdrawal Seizures

As with most AEDs, SUBVENITE should generally be withdrawn gradually because of the risk of increased seizure frequency and status epilepticus. In clinical trials in adults with bipolar disorder, 2 patients experienced seizures shortly after abrupt withdrawal of lamotrigine. The dosage of SUBVENITE should be tapered over a period of at least 2 weeks (approximately 50% reduction per week) [see Dosage and Administration (2.1)]. If withdrawal is needed because of a serious adverse reaction, rapid discontinuation can be considered.

5.11 Status Epilepticus

Valid estimates of the incidence of treatment-emergent status epilepticus among patients treated with lamotrigine are difficult to obtain because reporters participating in clinical trials did not all employ identical rules for identifying cases. At a minimum, 7 of 2,343 adult patients had episodes that could unequivocally be described as status epilepticus. In addition, a number of reports of variably defined episodes of seizure exacerbation (e.g., seizure clusters, seizure flurries) were made.

5.12 Addition of Lamotrigine to a Multidrug Regimen that Includes Valproate

Because valproate reduces the clearance of lamotrigine, the dosage of SUBVENITE in the presence of valproate is less than half of that required in its absence [see Dosage and Administration (2.2, 2.3, 2.4), Drug Interactions (7)].

5.13 Binding in the Eye and Other Melanin-Containing Tissues

Because lamotrigine binds to melanin, it could accumulate in melanin-rich tissues over time. This raises the possibility that SUBVENITE may cause toxicity in these tissues after extended use. Although ophthalmological testing was performed in one controlled clinical trial, the testing was inadequate to exclude subtle effects or injury occurring after long-term exposure. Moreover, the capacity of available tests to detect potentially adverse consequences, if any, of lamotrigine's binding to melanin is unknown [see Clinical Pharmacology (12.2)].

Accordingly, although there are no specific recommendations for periodic ophthalmological monitoring, prescribers should be aware of the possibility of long-term ophthalmologic effects.

5.14 Laboratory Tests

False-Positive Drug Test Results

Lamotrigine has been reported to interfere with the assay used in some rapid urine drug screens, which can result in false-positive readings, particularly for phencyclidine (PCP). A more specific analytical method should be used to confirm a positive result.

6 ADVERSE REACTIONS

The following serious adverse reactions are described in more detail elsewhere in the labeling:

- Serious Skin Rashes [see Boxed Warning and Warnings and Precautions (5.1)]
- Hemophagocytic Lymphohistiocytosis [see Warnings and Precautions (5.2)]
- Drug Reaction with Eosinophilia and Systemic Symptoms (DRESS)/Multiorgan Hypersensitivity [see Warnings and Precautions (5.3)]
- Cardiac Rhythm and Conduction Abnormalities [see Warnings and Precautions (5.4)]
- Blood Dyscrasias [see Warnings and Precautions (5.5)]
- Suicidal Behavior and Ideation [see Warnings and Precautions (5.6)]
- Aseptic Meningitis [see Warnings and Precautions (5.7)]
- Withdrawal Seizures [see Warnings and Precautions (5.10)]
- Status Epilepticus [see Warnings and Precautions (5.11)]

6.1 Clinical Trial Experience

The safety of SUBVENITE has been established from adequate and well-controlled studies that were conducted with other lamotrigine products in patients 2 years and older with epilepsy and in adults with bipolar disorder [see Clinical Studies (14.1, 14.2)]. Below is a display of the adverse reactions of lamotrigine in these adequate and well-controlled studies. Adverse reactions with SUBVENITE are expected to be similar to adverse reactions with other immediate-release lamotrigine products.

Because clinical trials are conducted under widely varying conditions, adverse reaction rates observed in the clinical trials of a drug cannot be directly compared with rates in the clinical trials of another drug and may not reflect the rates observed in practice.

Epilepsy

Most Common Adverse Reactions in All Clinical Trials: Adjunctive Therapy in Adults with Epilepsy: The most commonly observed (≥5% for lamotrigine and more common on drug than placebo) adverse reactions seen in association with lamotrigine during adjunctive therapy in adults and not seen at an equivalent frequency among placebo-treated patients were: dizziness, ataxia, somnolence, headache, diplopia, blurred vision, nausea, vomiting, and rash. Dizziness, diplopia, ataxia, blurred vision, nausea, and vomiting were dose related. Dizziness, diplopia, ataxia, and blurred vision occurred more commonly in patients receiving carbamazepine with lamotrigine than in patients receiving other AEDs with lamotrigine. Clinical data suggest a higher incidence of rash, including serious rash, in patients receiving concomitant valproate than in patients not receiving valproate [see Warnings and Precautions (5.1)].

Approximately 11% of the 3,378 adult patients who received lamotrigine as adjunctive therapy in premarketing clinical trials discontinued treatment because of an adverse reaction. The adverse reactions most commonly associated with discontinuation were rash (3.0%), dizziness (2.8%), and headache (2.5%).

In a dose-response trial in adults, the rate of discontinuation of lamotrigine for dizziness, ataxia, diplopia, blurred vision, nausea, and vomiting was dose related.

Monotherapy in Adults with Epilepsy: The most commonly observed (≥5% for lamotrigine and more common on drug than placebo) adverse reactions seen in association with the use of lamotrigine during the monotherapy phase of the controlled trial in adults not seen at an equivalent rate in the control group were vomiting, coordination abnormality, dyspepsia, nausea, dizziness, rhinitis, anxiety, insomnia, infection, pain, weight decrease, chest pain, and dysmenorrhea. The most commonly observed (≥5% for lamotrigine and more common on drug than placebo) adverse reactions associated with the use of lamotrigine during the conversion to monotherapy (add-on) period, not seen at an equivalent frequency among low-dose valproate-treated patients, were dizziness, headache, nausea, asthenia, coordination abnormality, vomiting, rash, somnolence, diplopia, ataxia, accidental injury, tremor, blurred vision, insomnia, nystagmus, diarrhea, lymphadenopathy, pruritus, and sinusitis.

Approximately 10% of the 420 adult patients who received lamotrigine as monotherapy in premarketing clinical trials discontinued treatment because of an adverse reaction. The adverse reactions most commonly associated with discontinuation were rash (4.5%), headache (3.1%), and asthenia (2.4%).

Adjunctive Therapy in Pediatric Patients with Epilepsy: The most commonly observed (≥5% for lamotrigine and more common on drug than placebo) adverse reactions seen in association with the use of lamotrigine as adjunctive treatment in pediatric patients aged 2 to 16 years and not seen at an equivalent rate in the control group were infection, vomiting, rash, fever, somnolence, accidental injury, dizziness, diarrhea, abdominal pain, nausea, ataxia, tremor, asthenia, bronchitis, flu syndrome, and diplopia.

In 339 patients aged 2 to 16 years with partial-onset seizures or generalized seizures of Lennox-Gastaut syndrome, 4.2% of patients on lamotrigine and 2.9% of patients on placebo discontinued due to adverse reactions. The most commonly reported adverse reaction that led to discontinuation of lamotrigine was rash.

Approximately 11.5% of the 1,081 pediatric patients aged 2 to 16 years who received lamotrigine as adjunctive therapy in premarketing clinical trials discontinued treatment because of an adverse reaction. The adverse reactions most commonly associated with discontinuation were rash (4.4%), reaction aggravated (1.7%), and ataxia (0.6%).

Controlled Adjunctive Clinical Trials in Adults with Epilepsy: Table 7 lists adverse reactions that occurred in adult patients with epilepsy treated with lamotrigine in placebo-controlled trials. In these trials, either lamotrigine or placebo was added to the patient’s current AED therapy.

Table 7. Adverse Reactions in Pooled, Placebo-Controlled Adjunctive Trials in Adult Patients with Epilepsya,b
Body System/Adverse Reaction | Percent of Patients Receiving Adjunctive Lamotrigine (n = 711) | Percent of Patients Receiving Adjunctive Placebo (n = 419)
Body as a whole Headache Flu syndrome Fever Abdominal pain Neck pain Reaction aggravated (seizure exacerbation) | 29 7 6 5 2 2 | 19 6 4 4 1 1
Digestive Nausea Vomiting Diarrhea Dyspepsia Constipation Anorexia | 19 9 6 5 4 2 | 10 4 4 2 3 1
Musculoskeletal Arthralgia | 2 | 0
Nervous Dizziness Ataxia Somnolence Incoordination Insomnia Tremor Depression Anxiety Convulsion Irritability Speech disorder Concentration disturbance | 38 22 14 6 6 4 4 4 3 3 3 2 | 13 6 7 2 2 1 3 3 1 2 0 1
Respiratory Rhinitis Pharyngitis Cough increased | 14 10 8 | 9 9 6
Skin and appendages Rash Pruritus | 10 3 | 5 2
Special senses Diplopia Blurred vision Vision abnormality | 28 16 3 | 7 5 1
Urogenital Female patients only Dysmenorrhea Vaginitis Amenorrhea | (n = 365) 7 4 2 | (n = 207) 6 1 1
a Adverse reactions that occurred in at least 2% of patients treated with lamotrigine and at a greater incidence than placebo.
b Patients in these adjunctive trials were receiving 1 to 3 of the concomitant AEDs carbamazepine, phenytoin, phenobarbital, or primidone in addition to lamotrigine or placebo. Patients may have reported multiple adverse reactions during the trial or at discontinuation; thus, patients may be included in more than 1 category.

In a randomized, parallel trial comparing placebo with 300 and 500 mg/day of lamotrigine, some of the more common drug-related adverse reactions were dose related (see Table 8).

Table 8. Dose-Related Adverse Reactions from a Randomized, Placebo-Controlled Adjunctive Trial in Adults with Epilepsy
 | Percent of Patients Experiencing Adverse Reactions
Adverse Reaction | Placebo (n = 73) | Lamotrigine; 300 mg (n = 71) | Lamotrigine; 500 mg (n = 72)
Ataxia Blurred vision Diplopia Dizziness Nausea Vomiting | 10 10 8 27 11 4 | 10 11 24a 31 18 11 | 28a,b 25a,b 49a,b 54a,b 25a 18a
a Significantly greater than placebo group (P<0.05).
b Significantly greater than group receiving lamotrigine 300 mg (P<0.05).

The overall adverse reaction profile for lamotrigine was similar between females and males and was independent of age. Because the largest non-Caucasian racial subgroup was only 6% of patients exposed to lamotrigine in placebo-controlled trials, there are insufficient data to support a statement regarding the distribution of adverse reaction reports by race. Generally, females receiving either lamotrigine as adjunctive therapy or placebo were more likely to report adverse reactions than males. The only adverse reaction for which the reports on lamotrigine were > 10% more frequent in females than males (without a corresponding difference by gender on placebo) was dizziness (difference = 16.5%). There was little difference between females and males in the rates of discontinuation of lamotrigine for individual adverse reactions.

Controlled Monotherapy Trial in Adults with Partial-Onset Seizures: Table 9 lists adverse reactions that occurred in patients with epilepsy treated with monotherapy with lamotrigine in a double-blind trial following discontinuation of either concomitant carbamazepine or phenytoin not seen at an equivalent frequency in the control group.

Table 9. Adverse Reactions in a Controlled Monotherapy Trial in Adult Patients with Partial-Onset Seizuresa,b
Body System/ Adverse Reaction | Percent of Patients Receiving Lamotrigine c as Monotherapyv (n = 43) | Percent of Patients Receiving Low-Dose Valproated Monotherapy (n = 44)
Body as a whole Pain Infection Chest pain | 5 5 5 | 0 2 2
Digestive Vomiting Dyspepsia Nausea | 9 7 7 | 0 2 2
Metabolic and nutritional Weight decrease | 5 | 2
Nervous Coordination abnormality Dizziness Anxiety Insomnia | 7 7 5 5 | 0 0 0 2
Respiratory Rhinitis | 7 | 2
Urogenital (female patients only) Dysmenorrhea | (n = 21) 5 | (n = 28) 0
a Adverse reactions that occurred in at least 5% of patients treated with lamotrigine and at a greater incidence than valproate-treated patients.
b Patients in this trial were converted to lamotrigine or valproate monotherapy from adjunctive therapy with carbamazepine or phenytoin. Patients may have reported multiple adverse reactions during the trial; thus, patients may be included in more than 1 category.
c Up to 500 mg/day.
d 1,000 mg/day.

Adverse reactions that occurred with a frequency of <5% and >2% of patients receiving lamotrigine and numerically more frequent than placebo were:

Body as a Whole: Asthenia, fever.

Digestive: Anorexia, dry mouth, rectal hemorrhage, peptic ulcer.

Metabolic and Nutritional: Peripheral edema.

Nervous System: Amnesia, ataxia, depression, hypesthesia, libido increase, decreased reflexes, increased reflexes, nystagmus, irritability, suicidal ideation.

Respiratory: Epistaxis, bronchitis, dyspnea.

Skin and Appendages: Contact dermatitis, dry skin, sweating.

Special Senses: Vision abnormality.

Incidence in Controlled Adjunctive Trials in Pediatric Patients with Epilepsy: Table 10 lists adverse reactions that occurred in 339 pediatric patients with partial-onset seizures or generalized seizures of Lennox-Gastaut syndrome who received lamotrigine up to 15 mg/kg/day or a maximum of 750 mg/day.

Table 10. Adverse Reactions in Pooled, Placebo-Controlled Adjunctive Trials in Pediatric Patients with Epilepsya
Body System/ Adverse Reaction | Percent of Patients Receiving Lamotrigine (n = 168) | Percent of Patients Receiving Placebo (n = 171)
Body as a whole Infection Fever Accidental injury Abdominal pain Asthenia Flu syndrome Pain Facial edema Photosensitivity | 20 15 14 10 8 7 5 2 2 | 17 14 12 5 4 6 4 1 0
Cardiovascular Hemorrhage | 2 | 1
Digestive Vomiting Diarrhea Nausea Constipation Dyspepsia | 20 11 10 4 2 | 16 9 2 2 1
Hemic and lymphatic Lymphadenopathy | 2 | 1
Metabolic and nutritional Edema | 2 | 0
Nervous system Somnolence Dizziness Ataxia Tremor Emotional lability Gait abnormality Thinking abnormality Convulsions Nervousness Vertigo | 17 14 11 10 4 4 3 2 2 2 | 15 4 3 1 2 2 2 1 1 1
Respiratory Pharyngitis Bronchitis Increased cough Sinusitis Bronchospasm | 14 7 7 2 2 | 11 5 6 1 1
Skin Rash Eczema Pruritus | 14 2 2 | 12 1 1
Special senses Diplopia Blurred vision Visual abnormality | 5 4 2 | 1 1 0
Urogenital Male and female patients Urinary tract infection | 3 | 0
a Adverse reactions that occurred in at least 2% of patients treated with lamotrigine and at a greater incidence than placebo.

Bipolar Disorder in Adults

The most common adverse reactions seen in association with the use of lamotrigine as monotherapy (100 to 400 mg/day) in adult patients (aged 18 to 82 years) with bipolar disorder in the 2 double-blind, placebo-controlled trials of 18 months’ duration are included in Table 11. Adverse reactions that occurred in at least 5% of patients and were numerically more frequent during the dose-escalation phase of lamotrigine in these trials (when patients may have been receiving concomitant medications) compared with the monotherapy phase were: headache (25%), rash (11%), dizziness (10%), diarrhea (8%), dream abnormality (6%), and pruritus (6%).

During the monotherapy phase of the double-blind, placebo-controlled trials of 18 months’ duration, 13% of 227 patients who received lamotrigine (100 to 400 mg/day), 16% of 190 patients who received placebo, and 23% of 166 patients who received lithium discontinued therapy because of an adverse reaction. The adverse reactions that most commonly led to discontinuation of lamotrigine were rash (3%) and mania/hypomania/mixed mood adverse reactions (2%). Approximately 16% of 2,401 patients who received lamotrigine (50 to 500 mg/day) for bipolar disorder in premarketing trials discontinued therapy because of an adverse reaction, most commonly due to rash (5%) and mania/hypomania/mixed mood adverse reactions (2%).

The overall adverse reaction profile for lamotrigine was similar between females and males, between elderly and nonelderly patients, and among racial groups.

Table 11. Adverse Reactions in 2 Placebo-Controlled Trials in Adult Patients with Bipolar I Disorder a,b
Body System/ Adverse Reaction | Percent of Patients Receiving Lamotrigine (n = 227) | Percent of Patients Receiving Placebo (n = 190)
General Back pain Fatigue Abdominal pain | 8 8 6 | 6 5 3
Digestive Nausea Constipation Vomiting | 14 5 5 | 11 2 2
Nervous System Insomnia Somnolence Xerostomia (dry mouth) | 10 9 6 | 6 7 4
Respiratory Rhinitis Exacerbation of cough Pharyngitis | 7 5 5 | 4 3 4
Skin Rash (nonserious)c | 7 | 5

a Adverse reactions that occurred in at least 5% of patients treated with lamotrigine and at a greater incidence than placebo.
b Patients in these trials were converted to lamotrigine (100 to 400 mg/day) or placebo monotherapy from add-on therapy with other psychotropic medications. Patients may have reported multiple adverse reactions during the trial; thus, patients may be included in more than 1 category.
c In the overall bipolar and other mood disorders clinical trials, the rate of serious rash was 0.08% (1 of 1,233) of adult patients who received lamotrigine as initial monotherapy and 0.13% (2 of 1,538) of adult patients who received lamotrigine as adjunctive therapy [see Warnings and Precautions (5.1)].

Other reactions that occurred in 5% or more patients but equally or more frequently in the placebo group included: dizziness, mania, headache, infection, influenza, pain, accidental injury, diarrhea, and dyspepsia.

Adverse reactions that occurred with a frequency of <5% and >1% of patients receiving lamotrigine and numerically more frequent than placebo were:

General: Fever, neck pain.

Cardiovascular: Migraine.

Digestive: Flatulence.

Metabolic and Nutritional: Weight gain, edema.

Musculoskeletal: Arthralgia, myalgia.

Nervous System: Amnesia, depression, agitation, emotional lability, dyspraxia, abnormal thoughts, dream abnormality, hypoesthesia.

Respiratory: Sinusitis.

Urogenital: Urinary frequency.

Adverse Reactions following Abrupt Discontinuation: In the 2 controlled clinical trials, there was no increase in the incidence, severity, or type of adverse reactions in patients with bipolar disorder after abruptly terminating therapy with lamotrigine. In the clinical development program in adults with bipolar disorder, 2 patients experienced seizures shortly after abrupt withdrawal of lamotrigine [see Warnings and Precautions (5.10)].

Mania/Hypomania/Mixed Episodes: During the double-blind placebo-controlled clinical trials in bipolar I disorder in which adults were converted to monotherapy with lamotrigine (100 to 400 mg/day) from other psychotropic medications and followed for up to 18 months, the rates of manic or hypomanic or mixed mood episodes reported as adverse reactions were 5% for patients treated with lamotrigine (n = 227), 4% for patients treated with lithium (n = 166), and 7% for patients treated with placebo (n = 190). In all bipolar controlled trials combined, adverse reactions of mania (including hypomania and mixed mood episodes) were reported in 5% of patients treated with lamotrigine (n = 956), 3% of patients treated with lithium (n = 280), and 4% of patients treated with placebo (n = 803).

6.2 Other Adverse Reactions Observed in All Clinical Trials

Lamotrigine has been administered to 6,694 individuals for whom complete adverse reaction data was captured during all clinical trials, only some of which were placebo controlled. During these trials, all adverse reactions were recorded by the clinical investigators using terminology of their own choosing. To provide a meaningful estimate of the proportion of individuals having adverse reactions, similar types of adverse reactions were grouped into a smaller number of standardized categories using modified COSTART dictionary terminology. The frequencies presented represent the proportion of the 6,694 individuals exposed to lamotrigine who experienced an event of the type cited on at least 1 occasion while receiving lamotrigine. All reported adverse reactions are included except those already listed in the previous tables or elsewhere in the labeling, those too general to be informative, and those not reasonably associated with the use of the drug.

Adverse reactions are further classified within body system categories and enumerated in order of decreasing frequency using the following definitions: frequent adverse reactions are defined as those occurring in at least 1/100 patients; infrequent adverse reactions are those occurring in 1/100 to 1/1,000 patients; rare adverse reactions are those occurring in fewer than 1/1,000 patients.

Body as a Whole

Infrequent: Allergic reaction, chills, malaise.

Cardiovascular System

Infrequent: Flushing, hot flashes, hypertension, palpitations, postural hypotension, syncope, tachycardia, vasodilation.

Dermatological

Infrequent: Acne, alopecia, hirsutism, maculopapular rash, skin discoloration, urticaria.

Rare: Angioedema, erythema, exfoliative dermatitis, fungal dermatitis, herpes zoster, leukoderma, multiforme erythema, petechial rash, pustular rash, Stevens-Johnson syndrome, vesiculobullous rash.

Digestive System

Infrequent: Dysphagia, eructation, gastritis, gingivitis, increased appetite, increased salivation, liver function tests abnormal, mouth ulceration.

Rare: Gastrointestinal hemorrhage, glossitis, gum hemorrhage, gum hyperplasia, hematemesis, hemorrhagic colitis, hepatitis, melena, stomach ulcer, stomatitis, tongue edema.

Endocrine System

Rare: Goiter, hypothyroidism.

Hematologic and Lymphatic System

Infrequent: Ecchymosis, leukopenia.

Rare: Anemia, eosinophilia, fibrin decrease, fibrinogen decrease, iron deficiency anemia, leukocytosis, lymphocytosis, macrocytic anemia, petechia, thrombocytopenia.

Metabolic and Nutritional Disorders

Infrequent: Aspartate transaminase increased.

Rare: Alcohol intolerance, alkaline phosphatase increase, alanine transaminase increase, bilirubinemia, general edema, gamma glutamyl transpeptidase increase, hyperglycemia.

Musculoskeletal System

Infrequent: Arthritis, leg cramps, myasthenia, twitching.

Rare: Bursitis, muscle atrophy, pathological fracture, tendinous contracture.

Nervous System

Frequent: Confusion, paresthesia.

Infrequent: Akathisia, apathy, aphasia, central nervous system depression, depersonalization, dysarthria, dyskinesia, euphoria, hallucinations, hostility, hyperkinesia, hypertonia, libido decreased, memory decrease, mind racing, movement disorder, myoclonus, panic attack, paranoid reaction, personality disorder, psychosis, sleep disorder, stupor, suicidal ideation.

Rare: Choreoathetosis, delirium, delusions, dysphoria, dystonia, extrapyramidal syndrome, faintness, grand mal convulsions, hemiplegia, hyperalgesia, hyperesthesia, hypokinesia, hypotonia, manic depression reaction, muscle spasm, neuralgia, neurosis, paralysis, peripheral neuritis.

Respiratory System

Infrequent: Yawn.

Rare: Hiccup, hyperventilation.

Special Senses

Frequent: Amblyopia.

Infrequent: Abnormality of accommodation, conjunctivitis, dry eyes, ear pain, photophobia, taste perversion, tinnitus.

Rare: Deafness, lacrimation disorder, oscillopsia, parosmia, ptosis, strabismus, taste loss, uveitis, visual field defect.

Urogenital System

Infrequent: Abnormal ejaculation, hematuria, impotence, menorrhagia, polyuria, urinary incontinence.

Rare: Acute kidney failure, anorgasmia, breast abscess, breast neoplasm, creatinine increase, cystitis, dysuria, epididymitis, female lactation, kidney failure, kidney pain, nocturia, urinary retention, urinary urgency.

6.3 Postmarketing Experience

The following adverse reactions have been identified during postapproval use of lamotrigine. Because these reactions are reported voluntarily from a population of uncertain size, it is not always possible to reliably estimate their frequency or establish a causal relationship to drug exposure.

Blood and Lymphatic

Agranulocytosis, hemolytic anemia, lymphadenopathy not associated with hypersensitivity disorder, pseudolymphoma.

Gastrointestinal

Esophagitis.

Hepatobiliary Tract and Pancreas

Pancreatitis.

Immunologic

Hypogammaglobulinemia, lupus-like reaction, vasculitis.

Lower Respiratory

Apnea.

Musculoskeletal

Rhabdomyolysis has been observed in patients experiencing hypersensitivity reactions.

Nervous System

Aggression, exacerbation of Parkinsonian symptoms in patients with pre-existing Parkinson’s disease, tics.

Non-site Specific

Progressive immunosuppression.

Renal and Urinary Disorders

Tubulointerstitial nephritis (has been reported alone and in association with uveitis).

Skin and Subcutaneous Tissue Disorders

Photosensitivity reaction.

7 DRUG INTERACTIONS

Significant drug interactions with SUBVENITE are summarized in this section.

Uridine 5´-diphospho-glucuronyl transferases (UGT) have been identified as the enzymes responsible for metabolism of lamotrigine, the active ingredient in SUBVENITE. Drugs that induce or inhibit glucuronidation may, therefore, affect the apparent clearance of lamotrigine. Strong or moderate inducers of the cytochrome P450 3A4 (CYP3A4) enzyme, which are also known to induce UGT, may also enhance the metabolism of lamotrigine.

Those drugs that have been demonstrated to have a clinically significant impact on lamotrigine metabolism are outlined in Table 12. Specific dosing guidance for these drugs is provided in the Dosage and Administration section, and, for women taking estrogen-containing products, including oral contraceptives, in the Warnings and Precautions section [see Dosage and Administration (2.1), Warnings and Precautions (5.9)].

Additional details of these drug interaction studies are provided in the Clinical Pharmacology section [see Clinical Pharmacology (12.3)].

Table 12. Established and Other Potentially Significant Drug Interactions with SUBVENITE
Concomitant Drug | Effect on Concentration of Lamotrigine or Concomitant Drug | Clinical Comment
Estrogen-containing oral contraceptive preparations containing 30 mcg ethinylestradiol and 150 mcg levonorgestrel | ↓ lamotrigine ↓ levonorgestrel | Decreased lamotrigine concentrations approximately 50%. Decrease in levonorgestrel component by 19%.
Carbamazepine and carbamazepine epoxide | ↓ lamotrigine ? carbamazepine epoxide | Addition of carbamazepine decreases lamotrigine concentration approximately 40%. May increase carbamazepine epoxide levels.
Lopinavir/ritonavir | ↓ lamotrigine | Decreased lamotrigine concentration approximately 50%.
Atazanavir/ritonavir | ↓ lamotrigine | Decreased lamotrigine AUC approximately 32%.
Phenobarbital/primidone | ↓ lamotrigine | Decreased lamotrigine concentration approximately 40%.
Phenytoin | ↓ lamotrigine | Decreased lamotrigine concentration approximately 40%.
Rifampin | ↓ lamotrigine | Decreased lamotrigine AUC approximately 40%.
Valproate | ↑ lamotrigine ? valproate | Increased lamotrigine concentrations slightly more than 2-fold. There are conflicting study results regarding effect of lamotrigine on valproate concentrations: 1) a mean 25% decrease in valproate concentrations in healthy volunteers, 2) no change in valproate concentrations in controlled clinical trials in patients with epilepsy.
↓= Decreased (induces lamotrigine glucuronidation).
↑= Increased (inhibits lamotrigine glucuronidation).
?= Conflicting data.

Effect of SUBVENITE on Organic Cationic Transporter 2 Substrates

Lamotrigine is an inhibitor of renal tubular secretion via organic cationic transporter 2 (OCT2) proteins [see Clinical Pharmacology (12.3)]. This may result in increased plasma levels of certain drugs that are substantially excreted via this route. Coadministration of SUBVENITE with OCT2 substrates with a narrow therapeutic index (e.g., dofetilide) is not recommended.

8 USE IN SPECIFIC POPULATIONS

8.1 Pregnancy

Pregnancy Exposure Registry

There is a pregnancy exposure registry that monitors pregnancy outcomes in women exposed to AEDs, including SUBVENITE, during pregnancy. Encourage women who are taking SUBVENITE during pregnancy to enroll in the North American Antiepileptic Drug (NAAED) Pregnancy Registry by calling 1-888-233-2334 or visiting http://www.aedpregnancyregistry.org/.

Risk Summary

Data from several prospective pregnancy exposure registries and epidemiological studies of pregnant women have not detected an increased frequency of major congenital malformations or a consistent pattern of malformations among women exposed to lamotrigine compared with the general population (see Data). The majority of lamotrigine pregnancy exposure data are from women with epilepsy. In animal studies, administration of lamotrigine during pregnancy resulted in developmental toxicity (increased mortality, decreased body weight, increased structural variation, neurobehavioral abnormalities) at doses lower than those administered clinically.

Lamotrigine decreased fetal folate concentrations in rats, an effect known to be associated with adverse pregnancy outcomes in animals and humans (see Data).

In the U.S. general population, the estimated background risk of major birth defects and miscarriage in clinically recognized pregnancies is 2% to 4% and 15% to 20%, respectively.

Clinical Considerations

Disease-associated Maternal and/or Embryofetal Risk

Epilepsy, with or without exposure to antiepileptic drugs, has been associated with several adverse outcomes during pregnancy, including preeclampsia, preterm labor, antepartum and postpartum hemorrhage, placental abruption, poor fetal growth, prematurity, fetal death, and maternal mortality. The risk of maternal or fetal injury may be greatest for patients with untreated or poorly controlled convulsive seizures. Women with epilepsy who become pregnant should not abruptly discontinue antiepileptic drugs, including SUBVENITE, due to the risk of status epilepticus or severe seizures, which may be life-threatening [see Warnings and Precautions (5.10)].

Dose Adjustments During Pregnancy and the Postpartum Period

As with other AEDs, physiological changes during pregnancy may affect lamotrigine concentrations and/or therapeutic effect. There have been reports of decreased lamotrigine concentrations during pregnancy and restoration of pre-pregnancy concentrations after delivery. Dose adjustments may be necessary to maintain clinical response.

Data

Human Data: Data from several international pregnancy registries have not shown an increased risk for malformations overall. The International Lamotrigine Pregnancy Registry reported major congenital malformations in 2.2% (95% CI: 1.6%, 3.1%) of 1,558 infants exposed to lamotrigine monotherapy in the first trimester of pregnancy. The NAAED Pregnancy Registry reported major congenital malformations among 2.0% of 1,562 infants exposed to lamotrigine monotherapy in the first trimester. EURAP, a large international pregnancy registry focused outside of North America, reported major birth defects in 2.9% (95% CI: 2.3%, 3.7%) of 2,514 exposures to lamotrigine monotherapy in the first trimester. The frequency of major congenital malformations was similar to estimates from the general population.

The NAAED Pregnancy Registry observed an increased risk of isolated oral clefts: among 2,200 infants exposed to lamotrigine early in pregnancy, the risk of oral clefts was 3.2 per 1,000 (95% CI: 1.4, 6.3), a 3-fold increased risk versus unexposed healthy controls. This finding has not been observed in other large international pregnancy registries. Furthermore, a case-control study based on 21 congenital anomaly registries covering over 10 million births in Europe reported an adjusted odds ratio for isolated oral clefts with lamotrigine exposure of 1.45 (95% CI: 0.8, 2.63).

Several meta-analyses have not reported an increased risk of major congenital malformations following lamotrigine exposure in pregnancy compared with healthy and disease-matched controls. No patterns of specific malformation types were observed.

The same meta-analyses evaluated the risk of additional maternal and infant outcomes including fetal death, stillbirth, preterm birth, small for gestational age, and neurodevelopmental delay. Although there are no data suggesting an increased risk of these outcomes with lamotrigine monotherapy exposure, differences in outcome definition, ascertainment methods, and comparator groups limit the conclusions that can be drawn.

Animal Data: When lamotrigine was administered to pregnant mice, rats, or rabbits during the period of organogenesis (oral doses of up to 125, 25, and 30 mg/kg, respectively), reduced fetal body weight and increased incidences of fetal skeletal variations were seen in mice and rats at doses that were also maternally toxic. The no-effect doses for embryofetal developmental toxicity in mice, rats, and rabbits (75, 6.25, and 30 mg/kg, respectively) are similar to (mice and rabbits) or less than (rats) the human dose of 400 mg/day on a body surface area (mg/m^2) basis.

In a study in which pregnant rats were administered lamotrigine (oral doses of 0, 5, or 25 mg/kg) during the period of organogenesis and offspring were evaluated postnatally, neurobehavioral abnormalities were observed in exposed offspring at both doses. The lowest effect dose for developmental neurotoxicity in rats is less than the human dose of 400 mg/day on a mg/m2 basis. Maternal toxicity was observed at the higher dose tested.

When pregnant rats were administered lamotrigine (oral doses of 0, 5, 10, or 20 mg/kg) during the latter part of gestation and throughout lactation, increased offspring mortality (including stillbirths) was seen at all doses. The lowest effect dose for pre- and post-natal developmental toxicity in rats is less than the human dose of 400 mg/day on a mg/m^2 basis. Maternal toxicity was observed at the 2 highest doses tested.

When administered to pregnant rats, lamotrigine decreased fetal folate concentrations at doses greater than or equal to 5 mg/kg/day, which is less than the human dose of 400 mg/day on a mg/m^2 basis.

8.2 Lactation

Risk Summary

Lamotrigine is present in milk from lactating women taking lamotrigine (see Data). Neonates and young infants are at risk for high serum levels because maternal serum and milk levels can rise to high levels postpartum if lamotrigine dosage has been increased during pregnancy but is not reduced after delivery to the pre-pregnancy dosage. Glucuronidation is required for drug clearance. Glucuronidation capacity is immature in the infant and this may also contribute to the level of lamotrigine exposure. Events including rash, apnea, drowsiness, poor sucking, and poor weight gain (requiring hospitalization in some cases) have been reported in infants who have been human milk-fed by mothers using lamotrigine; whether or not these events were caused by lamotrigine is unknown. No data are available on the effects of the drug on milk production.

The developmental and health benefits of breastfeeding should be considered along with the mother’s clinical need for SUBVENITE and any potential adverse effects on the breastfed infant from SUBVENITE or from the underlying maternal condition.

Clinical Considerations

Human milk-fed infants should be closely monitored for adverse events resulting from lamotrigine. Measurement of infant serum levels should be performed to rule out toxicity if concerns arise. Human milk-feeding should be discontinued in infants with lamotrigine toxicity.

Data

Data from multiple small studies indicate that lamotrigine plasma levels in nursing infants have been reported to be as high as 50% of maternal plasma concentrations.

8.4 Pediatric Use

Epilepsy

SUBVENITE is indicated as adjunctive therapy in patients aged 2 years and older for partial-onset seizures, the generalized seizures of Lennox-Gastaut syndrome, and PGTC seizures.

Safety and efficacy of lamotrigine used as adjunctive treatment for partial-onset seizures were not demonstrated in a small, randomized, double-blind, placebo-controlled withdrawal trial in very young pediatric patients (aged 1 to 24 months). Lamotrigine was associated with an increased risk for infectious adverse reactions (lamotrigine 37%, Placebo 5%), and respiratory adverse reactions (lamotrigine 26%, Placebo 5%). Infectious adverse reactions included bronchiolitis, bronchitis, ear infection, eye infection, otitis externa, pharyngitis, urinary tract infection, and viral infection. Respiratory adverse reactions included nasal congestion, cough, and apnea.

Bipolar Disorder

Safety and efficacy of lamotrigine for the maintenance treatment of bipolar disorder were not established in a double-blind, randomized withdrawal, placebo-controlled trial that evaluated 301 pediatric patients aged 10 to 17 years with a current manic/hypomanic, depressed, or mixed mood episode as defined by DSM-IV-TR. In the randomized phase of the trial, adverse reactions that occurred in at least 5% of patients taking lamotrigine (n = 87) and were twice as common compared with patients taking placebo (n = 86) were influenza (lamotrigine 8%, placebo 2%), oropharyngeal pain (lamotrigine 8%, placebo 2%), vomiting (lamotrigine 6%, placebo 2%), contact dermatitis (lamotrigine 5%, placebo 2%), upper abdominal pain (lamotrigine 5%, placebo 1%), and suicidal ideation (lamotrigine 5%, placebo 0%).

Juvenile Animal Data

In a juvenile animal study in which lamotrigine (oral doses of 0, 5, 15, or 30 mg/kg) was administered to young rats from postnatal day 7 to 62, decreased viability and growth were seen at the highest dose tested and long-term neurobehavioral abnormalities (decreased locomotor activity, increased reactivity, and learning deficits in animals tested as adults) were observed at the 2 highest doses. The no-effect dose for adverse developmental effects in juvenile animals is less than the human dose of 400 mg/day on a mg/m^2 basis.

8.5 Geriatric Use

Clinical trials of lamotrigine for epilepsy and bipolar disorder did not include sufficient numbers of patients aged 65 years and older to determine whether they respond differently from younger patients or exhibit a different safety profile than that of younger patients. In general, dose selection for an elderly patient should be cautious, usually starting at the low end of the dosing range, reflecting the greater frequency of decreased hepatic, renal, or cardiac function and of concomitant disease or other drug therapy.

8.6 Hepatic Impairment

Experience in patients with hepatic impairment is limited. Based on a clinical pharmacology study in 24 subjects with mild, moderate, and severe liver impairment, the following general recommendations can be made [see Clinical Pharmacology (12.3)]. No dosage adjustment is needed in patients with mild liver impairment. Initial, escalation, and maintenance doses should generally be reduced by approximately 25% in patients with moderate and severe liver impairment without ascites and 50% in patients with severe liver impairment with ascites. Escalation and maintenance doses may be adjusted according to clinical response [see Dosage and Administration (2.1)].

8.7 Renal Impairment

Lamotrigine is metabolized mainly by glucuronic acid conjugation, with the majority of the metabolites being recovered in the urine. In a small study comparing a single dose of lamotrigine in subjects with varying degrees of renal impairment with healthy volunteers, the plasma half-life of lamotrigine was approximately twice as long in the subjects with chronic renal failure [see Clinical Pharmacology (12.3)].

Initial doses of SUBVENITE should be based on patients' AED regimens; reduced maintenance doses may be effective for patients with significant renal impairment. Few patients with severe renal impairment have been evaluated during chronic treatment with lamotrigine. Because there is inadequate experience in this population, SUBVENITE should be used with caution in these patients [see Dosage and Administration (2.1)].

10 OVERDOSAGE

10.1 Human Overdose Experience

Overdoses involving quantities up to 15 g have been reported for lamotrigine, some of which have been fatal. Overdose has resulted in ataxia, nystagmus, seizures (including tonic-clonic seizures), decreased level of consciousness, coma, and intraventricular conduction delay.

10.2 Management of Overdose

There are no specific antidotes for lamotrigine. Following a suspected overdose, hospitalization of the patient is advised. General supportive care is indicated, including frequent monitoring of vital signs and close observation of the patient. If indicated, emesis should be induced; usual precautions should be taken to protect the airway. It should be kept in mind that immediate-release lamotrigine is rapidly absorbed [see Clinical Pharmacology (12.3)]. It is uncertain whether hemodialysis is an effective means of removing lamotrigine from the blood. In 6 renal failure patients, about 20% of the amount of lamotrigine in the body was removed by hemodialysis during a 4-hour session. A Poison Control Center should be contacted for information on the management of overdosage of SUBVENITE.

11 DESCRIPTION

SUBVENITE (lamotrigine) oral suspension, an AED of the phenyltriazine class, is chemically unrelated to existing AEDs. Lamotrigine’s chemical name is 3,5-diamino-6-(2,3-dichlorophenyl)-as-triazine, its molecular formula is C9H7N5Cl2, and its molecular weight is 256.09. Lamotrigine, USP is a white to pale cream-colored powder and has a pKa of 5.7. Lamotrigine, USP is very slightly soluble in water (0.17 mg/mL at 25°C) and slightly soluble in 0.1 M HCl (4.1 mg/mL at 25°C). The structural formula is:

SUBVENITE oral suspension contains 10 mg per mL lamotrigine, USP and the following inactive ingredients: carboxymethylcellulose sodium, cherry flavor, FD&C Red 40, FD&C Yellow 6, glycerin, methylparaben, polyethylene glycol, propylene glycol, purified water, saccharin sodium, silicified microcrystalline cellulose, sodium benzoate, sodium phosphate dibasic, sorbitol solution, sucralose and xanthan gum.

12 CLINICAL PHARMACOLOGY

12.1 Mechanism of Action

The precise mechanism(s) by which lamotrigine exerts its anticonvulsant action are unknown. In animal models designed to detect anticonvulsant activity, lamotrigine was effective in preventing seizure spread in the maximum electroshock (MES) and pentylenetetrazol (scMet) tests, and prevented seizures in the visually and electrically evoked after-discharge (EEAD) tests for antiepileptic activity. Lamotrigine also displayed inhibitory properties in the kindling model in rats both during kindling development and in the fully kindled state. The relevance of these models to human epilepsy, however, is not known.

One proposed mechanism of action of lamotrigine, the relevance of which remains to be established in humans, involves an effect on sodium channels. In vitro pharmacological studies suggest that lamotrigine inhibits voltage-sensitive sodium channels, thereby stabilizing neuronal membranes and consequently modulating presynaptic transmitter release of excitatory amino acids (e.g., glutamate and aspartate).

Effect of Lamotrigine on N-Methyl d-Aspartate-Receptor-Mediated Activity

Lamotrigine did not inhibit N-methyl d-aspartate (NMDA)-induced depolarizations in rat cortical slices or NMDA-induced cyclic GMP formation in immature rat cerebellum, nor did lamotrigine displace compounds that are either competitive or noncompetitive ligands at this glutamate receptor complex (CNQX, CGS, TCHP). The IC50 for lamotrigine effects on NMDA-induced currents (in the presence of 3 µM of glycine) in cultured hippocampal neurons exceeded 100 µM.

The mechanisms by which lamotrigine exerts its therapeutic action in bipolar disorder have not been established.

12.2 Pharmacodynamics

Folate Metabolism

In vitro, lamotrigine inhibited dihydrofolate reductase, the enzyme that catalyzes the reduction of dihydrofolate to tetrahydrofolate. Inhibition of this enzyme may interfere with the biosynthesis of nucleic acids and proteins. When oral daily doses of lamotrigine were given to pregnant rats during organogenesis, fetal, placental, and maternal folate concentrations were reduced. Significantly reduced concentrations of folate are associated with teratogenesis [see Use in Specific Populations (8.1)]. Folate concentrations were also reduced in male rats given repeated oral doses of lamotrigine. Reduced concentrations were partially returned to normal when supplemented with folinic acid.

Cardiac Electrophysiology

Effect of Lamotrigine: In vitro studies show that lamotrigine exhibits Class IB antiarrhythmic activity at therapeutically relevant concentrations. It inhibits human cardiac sodium channels with rapid onset and offset kinetics and strong voltage dependence, consistent with other Class IB antiarrhythmic agents. At therapeutic doses, lamotrigine did not slow ventricular conduction (widen QRS) in healthy individuals in a thorough QT study; however, in patients with clinically important structural or functional heart disease or with elevated heart rates, SUBVENITE could slow ventricular conduction [see Warnings and Precautions (5.4)].

Effect of Lamotrigine Metabolite: In dogs, lamotrigine is extensively metabolized to a 2-N- methyl metabolite. This metabolite causes dose-dependent prolongation of the PR interval, widening of the QRS complex, and, at higher doses, complete AV conduction block. The in vitro electrophysiological effects of this metabolite have not been studied. Similar cardiovascular effects from this metabolite are not anticipated in humans because only trace amounts of the 2-N-methyl metabolite (<0.6% of lamotrigine dose) have been found in human urine [see Clinical Pharmacology (12.3)]. However, it is conceivable that plasma concentrations of this metabolite could be increased in patients with a reduced capacity to glucuronidate lamotrigine (e.g., in patients with liver disease, patients taking concomitant medications that inhibit glucuronidation).

Accumulation in Kidneys

Lamotrigine accumulated in the kidney of the male rat, causing chronic progressive nephrosis, necrosis, and mineralization. These findings are attributed to α-2 microglobulin, a species- and sex-specific protein that has not been detected in humans or other animal species.

Melanin Binding

Lamotrigine binds to melanin-containing tissues, e.g., in the eye and pigmented skin. It has been found in the uveal tract up to 52 weeks after a single dose in rodents.

12.3 Pharmacokinetics

The pharmacokinetics of lamotrigine have been studied in subjects with epilepsy, healthy young and elderly volunteers, and volunteers with chronic renal failure. A pharmacokinetic study in heathy adult subjects under fasting conditions at a single 100 mg dose level demonstrated similar bioavailability for lamotrigine oral suspension and oral tablet.

Absorption

Lamotrigine is rapidly and completely absorbed after oral administration with negligible first-pass metabolism (absolute bioavailability is 98%). The bioavailability is not affected by food, but the time to reach maximum plasma concentrations is delayed by 3h in presence of food [see Dosage and Administration (2.5)].

Dose Proportionality

In healthy volunteers not receiving any other medications and given single doses, the plasma concentrations of lamotrigine increased in direct proportion to the dose administered over the range of 50 mg to 400 mg. In 2 small studies (n = 7 and 8) of patients with epilepsy who were maintained on other AEDs, there also was a linear relationship between dose and lamotrigine plasma concentrations at steady state following doses of 50 mg to 350 mg twice daily.

Distribution

Estimates of the mean apparent volume of distribution (Vd/F) of lamotrigine following oral administration ranged from 0.9 to 1.3 L/kg. Vd/F is independent of dose and is similar following single and multiple doses in both patients with epilepsy and in healthy volunteers.

Protein Binding

Data from in vitro studies indicate that lamotrigine is approximately 55% bound to human plasma proteins at plasma lamotrigine concentrations from 1 to 10 mcg/mL (10 mcg/mL is 4 to 6 times the trough plasma concentration observed in the controlled efficacy trials). Because lamotrigine is not highly bound to plasma proteins, clinically significant interactions with other drugs through competition for protein binding sites are unlikely. The binding of lamotrigine to plasma proteins did not change in the presence of therapeutic concentrations of phenytoin, phenobarbital, or valproate. Lamotrigine did not displace other AEDs (carbamazepine, phenytoin, phenobarbital) from protein-binding sites.

Metabolism

Lamotrigine is metabolized predominantly by glucuronic acid conjugation; the major metabolite is an inactive 2-N-glucuronide conjugate. After oral administration of 240 mg of ^14C-lamotrigine (15 μCi) to 6 healthy volunteers, 94% was recovered in the urine and 2% was recovered in the feces. The radioactivity in the urine consisted of unchanged lamotrigine (10%), the 2-N-glucuronide (76%), a 5-N-glucuronide (10%), a 2-N-methyl metabolite (0.14%), and other unidentified minor metabolites (4%).

Enzyme Induction

The effects of lamotrigine on the induction of specific families of mixed-function oxidase isozymes have not been systematically evaluated.

Following multiple administrations (150 mg twice daily) to normal volunteers taking no other medications, lamotrigine induced its own metabolism, resulting in a 25% decrease in t½ and a 37% increase in CL/F at steady state compared with values obtained in the same volunteers following a single dose. Evidence gathered from other sources suggests that self-induction by lamotrigine may not occur when lamotrigine is given as adjunctive therapy in patients receiving enzyme-inducing drugs such as carbamazepine, phenytoin, phenobarbital, primidone, or other drugs such as rifampin and the protease inhibitors lopinavir/ritonavir and atazanavir/ritonavir that induce lamotrigine glucuronidation [see Drug Interactions (7)].

Elimination

The mean elimination half-life of lamotrigine following multiple oral doses in adult patients with epilepsy is approximately 32 hours (range 8.5 hours to 49 hours), but the half-life and apparent oral clearance vary depending on concomitant AEDs.

Drug Interactions

The apparent clearance of lamotrigine is affected by the coadministration of certain medications [see Warnings and Precautions (5.9, 5.12), Drug Interactions (7)].

The net effects of drug interactions with lamotrigine are summarized in Table 13, followed by details of the drug interaction studies below.

Table 13. Summary of Drug Interactions with Lamotrigine
Drug | Drug Plasma Concentration with Adjunctive Lamotriginea | Lamotrigine Plasma Concentration with Adjunctive Drugsb
Oral contraceptives (e.g., ethinylestradiol / levonorgestrel)c | ↔d | ↓
Aripiprazole | Not assessed | ↔e
Atazanavir/ritonavir | ↔f | ↓
Bupropion | Not assessed | ↔
Carbamazepine | ↔ | ↓
Carbamazepine epoxideg | ?
Felbamate | Not assessed | ↔
Gabapentin | Not assessed | ↔
Lacosamide | Not assessed | ↔
Levetiracetam | ↔ | ↔
Lithium | ↔ | Not assessed
Lopinavir/ritonavir | ↔e | ↓
Olanzapine | ↔ | ↔e
Oxcarbazepine | ↔ | ↔
10-Monohydroxy oxcarbazepine metaboliteh | ↔
Perampanel | Not assessed | ↔e
Phenobarbital/primidone | ↔ | ↓
Phenytoin | ↔ | ↓
Pregabalin | ↔ | ↔
Rifampin | Not assessed | ↓
Risperidone | ↔ | Not assessed
9-Hydroxyrisperidonei | ↔
Topiramate | ↔j | ↔
Valproate | ↓ | ↑
Valproate + phenytoin and/or | Not assessed | ↔
carbamazepine
Zonisamide | Not assessed | ↔
a From adjunctive clinical trials and volunteer trials.
b Net effects were estimated by comparing the mean clearance values obtained in adjunctive clinical trials and volunteer trials.
c The effect of other hormonal contraceptive preparations or hormone replacement therapy on the pharmacokinetics of lamotrigine has not been systematically evaluated in clinical trials, although the effect may be similar to that seen with the ethinylestradiol/levonorgestrel combinations.
d Modest decrease in levonorgestrel.
e Slight decrease, not expected to be clinically meaningful.
f Compared with historical controls.
g Not administered, but an active metabolite of carbamazepine.
h Not administered, but an active metabolite of oxcarbazepine.
i Not administered, but an active metabolite of risperidone.
j Slight increase, not expected to be clinically meaningful.
↔ = No significant effect.
? = Conflicting data.

Estrogen-Containing Oral Contraceptives

In 16 female volunteers, an oral contraceptive preparation containing 30 mcg ethinylestradiol and 150 mcg levonorgestrel increased the apparent clearance of lamotrigine (300 mg/day) by approximately 2-fold with mean decreases in AUC of 52% and in Cmax of 39%. In this study, trough serum lamotrigine concentrations gradually increased and were approximately 2-fold higher on average at the end of the week of the inactive hormone preparation compared with trough lamotrigine concentrations at the end of the active hormone cycle.

Gradual transient increases in lamotrigine plasma levels (approximate 2-fold increase) occurred during the week of inactive hormone preparation (pill-free week) for women not also taking a drug that increased the clearance of lamotrigine (carbamazepine, phenytoin, phenobarbital, primidone, or other drugs such as rifampin and the protease inhibitors lopinavir/ritonavir and atazanavir/ritonavir that induce lamotrigine glucuronidation) [see Drug Interactions (7)]. The increase in lamotrigine plasma levels will be greater if the dose of SUBVENITE is increased in the few days before or during the pill-free week. Increases in lamotrigine plasma levels could result in dose-dependent adverse reactions.

In the same study, coadministration of lamotrigine (300 mg/day) in 16 female volunteers did not affect the pharmacokinetics of the ethinylestradiol component of the oral contraceptive preparation. There were mean decreases in the AUC and Cmax of the levonorgestrel component of 19% and 12%, respectively. Measurement of serum progesterone indicated that there was no hormonal evidence of ovulation in any of the 16 volunteers, although measurement of serum FSH, LH, and estradiol indicated that there was some loss of suppression of the hypothalamic-pituitary-ovarian axis.

The effects of doses of lamotrigine other than 300 mg/day have not been systematically evaluated in controlled clinical trials. Studies with other female hormonal preparations (including progesterone/progesterone-containing HRT) have not been conducted.

Dosage adjustments may be necessary for women receiving estrogen-containing products, including oral contraceptive preparations [see Dosage and Administration (2.1)].

Other Hormonal Contraceptives or Hormone Replacement Therapy

The effect of other hormonal contraceptive preparations or hormone replacement therapy on the pharmacokinetics of lamotrigine has not been systematically evaluated. It has been reported that ethinylestradiol, not progestogens, increased the clearance of lamotrigine up to 2-fold, and the progestin-only pills had no effect on lamotrigine plasma levels. Therefore, adjustments to the dosage of SUBVENITE in the presence of progestogens alone will likely not be needed.

Aripiprazole

In 18 patients with bipolar disorder on a stable regimen of 100 to 400 mg/day of lamotrigine, the lamotrigine AUC and Cmax were reduced by approximately 10% in patients who received aripiprazole 10 to 30 mg/day for 7 days, followed by 30 mg/day for an additional 7 days. This reduction in lamotrigine exposure is not considered clinically meaningful.

Atazanavir/Ritonavir

In a study in healthy volunteers, daily doses of atazanavir/ritonavir (300 mg/100 mg) reduced the plasma AUC and Cmax of lamotrigine (single 100-mg dose) by an average of 32% and 6%, respectively, and shortened the elimination half-lives by 27%. In the presence of atazanavir/ritonavir (300 mg/100 mg), the metabolite-to-lamotrigine ratio was increased from 0.45 to 0.71 consistent with induction of glucuronidation. The pharmacokinetics of atazanavir/ritonavir were similar in the presence of concomitant lamotrigine to the historical data of the pharmacokinetics in the absence of lamotrigine.

Bupropion

The pharmacokinetics of a 100-mg single dose of lamotrigine in healthy volunteers (n = 12) were not changed by coadministration of bupropion sustained-release formulation (150 mg twice daily) starting 11 days before lamotrigine.

Carbamazepine

Lamotrigine has no appreciable effect on steady-state carbamazepine plasma concentration. Limited clinical data suggest there is a higher incidence of dizziness, diplopia, ataxia, and blurred vision in patients receiving carbamazepine with lamotrigine than in patients receiving other AEDs with lamotrigine [see Adverse Reactions (6.1)]. The mechanism of this interaction is unclear. The effect of lamotrigine on plasma concentrations of carbamazepine-epoxide is unclear. In a small subset of patients (n = 7) studied in a placebo-controlled trial, lamotrigine had no effect on carbamazepine-epoxide plasma concentrations, but in a small, uncontrolled study (n = 9), carbamazepine-epoxide levels increased.

The addition of carbamazepine decreases lamotrigine steady-state concentrations by approximately 40%.

Felbamate

In a trial in 21 healthy volunteers, coadministration of felbamate (1,200 mg twice daily) with lamotrigine (100 mg twice daily for 10 days) appeared to have no clinically relevant effects on the pharmacokinetics of lamotrigine.

Folate Inhibitors

Lamotrigine is a weak inhibitor of dihydrofolate reductase. Prescribers should be aware of this action when prescribing other medications that inhibit folate metabolism.

Gabapentin

Based on a retrospective analysis of plasma levels in 34 subjects who received lamotrigine both with and without gabapentin, gabapentin does not appear to change the apparent clearance of lamotrigine.

Lacosamide

Plasma concentrations of lamotrigine were not affected by concomitant lacosamide (200, 400, or 600 mg/day) in placebo-controlled clinical trials in patients with partial-onset seizures.

Levetiracetam

Potential drug interactions between levetiracetam and lamotrigine were assessed by evaluating serum concentrations of both agents during placebo-controlled clinical trials. These data indicate that lamotrigine does not influence the pharmacokinetics of levetiracetam and that levetiracetam does not influence the pharmacokinetics of lamotrigine.

Lithium

The pharmacokinetics of lithium were not altered in healthy subjects (n = 20) by coadministration of lamotrigine (100 mg/day) for 6 days.

Lopinavir/Ritonavir

The addition of lopinavir (400 mg twice daily)/ritonavir (100 mg twice daily) decreased the AUC, Cmax, and elimination half-life of lamotrigine by approximately 50% to 55.4% in 18 healthy subjects. The pharmacokinetics of lopinavir/ritonavir were similar with concomitant lamotrigine, compared with that in historical controls.

Olanzapine

The AUC and Cmax of olanzapine were similar following the addition of olanzapine (15 mg once daily) to lamotrigine (200 mg once daily) in healthy male volunteers (n = 16) compared with the AUC and Cmax in healthy male volunteers receiving olanzapine alone (n = 16).

In the same trial, the AUC and Cmax of lamotrigine were reduced on average by 24% and 20%, respectively, following the addition of olanzapine to lamotrigine in healthy male volunteers compared with those receiving lamotrigine alone. This reduction in lamotrigine plasma concentrations is not expected to be clinically meaningful.

Oxcarbazepine

The AUC and Cmax of oxcarbazepine and its active 10-monohydroxy oxcarbazepine metabolite were not significantly different following the addition of oxcarbazepine (600 mg twice daily) to lamotrigine (200 mg once daily) in healthy male volunteers (n = 13) compared with healthy male volunteers receiving oxcarbazepine alone (n = 13).

In the same trial, the AUC and Cmax of lamotrigine were similar following the addition of oxcarbazepine (600 mg twice daily) to lamotrigine in healthy male volunteers compared with those receiving lamotrigine alone. Limited clinical data suggest a higher incidence of headache, dizziness, nausea, and somnolence with coadministration of lamotrigine and oxcarbazepine compared with lamotrigine alone or oxcarbazepine alone.

Perampanel

In a pooled analysis of data from 3 placebo-controlled clinical trials investigating adjunctive perampanel in patients with partial-onset and PGTC seizures, the highest perampanel dose evaluated (12 mg/day) increased lamotrigine clearance by <10%. An effect of this magnitude is not considered to be clinically relevant.

Phenobarbital, Primidone

The addition of phenobarbital or primidone decreases lamotrigine steady-state concentrations by approximately 40%.

Phenytoin

Lamotrigine has no appreciable effect on steady-state phenytoin plasma concentrations in patients with epilepsy. The addition of phenytoin decreases lamotrigine steady-state concentrations by approximately 40%.

Pregabalin

Steady-state trough plasma concentrations of lamotrigine were not affected by concomitant pregabalin (200 mg 3 times daily) administration. There are no pharmacokinetic interactions between lamotrigine and pregabalin.

Rifampin

In 10 male volunteers, rifampin (600 mg/day for 5 days) significantly increased the apparent clearance of a single 25-mg dose of lamotrigine by approximately 2-fold (AUC decreased by approximately 40%).

Risperidone

In a 14 healthy volunteers study, multiple oral doses of lamotrigine 400 mg daily had no clinically significant effect on the single-dose pharmacokinetics of risperidone 2 mg and its active metabolite 9-OH risperidone. Following the coadministration of risperidone 2 mg with lamotrigine, 12 of the 14 volunteers reported somnolence compared with 1 out of 20 when risperidone was given alone, and none when lamotrigine was administered alone.

Topiramate

Topiramate resulted in no change in plasma concentrations of lamotrigine. Administration of lamotrigine resulted in a 15% increase in topiramate concentrations.

Valproate

When lamotrigine was administered to healthy volunteers (n = 18) receiving valproate, the trough steady-state valproate plasma concentrations decreased by an average of 25% over a 3-week period, and then stabilized. However, adding lamotrigine to the existing therapy did not cause a change in valproate plasma concentrations in either adult or pediatric patients in controlled clinical trials.

The addition of valproate increased lamotrigine steady-state concentrations in normal volunteers by slightly more than 2-fold. In 1 trial, maximal inhibition of lamotrigine clearance was reached at valproate doses between 250 and 500 mg/day and did not increase as the valproate dose was further increased.

Zonisamide

In a study in 18 patients with epilepsy, coadministration of zonisamide (200 to 400 mg/day) with lamotrigine (150 to 500 mg/day for 35 days) had no significant effect on the pharmacokinetics of lamotrigine.

Known Inducers or Inhibitors of Glucuronidation

Drugs other than those listed above have not been systematically evaluated in combination with lamotrigine. Since lamotrigine is metabolized predominately by glucuronic acid conjugation, drugs that are known to induce or inhibit glucuronidation may affect the apparent clearance of lamotrigine and doses of lamotrigine may require adjustment based on clinical response.

Other

In vitro assessment of the inhibitory effect of lamotrigine at OCT2 demonstrate that lamotrigine, but not the N(2)-glucuronide metabolite, is an inhibitor of OCT2 at potentially clinically relevant concentrations, with IC50 value of 53.8 μM [see Drug Interactions (7)].

Results of in vitro experiments suggest that clearance of lamotrigine is unlikely to be reduced by concomitant administration of amitriptyline, clonazepam, clozapine, fluoxetine, haloperidol, lorazepam, phenelzine, sertraline, or trazodone.

Results of in vitro experiments suggest that lamotrigine does not reduce the clearance of drugs eliminated predominantly by CYP2D6.

Specific Populations

Patients with Renal Impairment: Twelve volunteers with chronic renal failure (mean creatinine clearance: 13 mL/min, range: 6 to 23) and another 6 individuals undergoing hemodialysis were each given a single 100-mg dose of lamotrigine. The mean plasma half-lives determined in the study were 42.9 hours (chronic renal failure), 13.0 hours (during hemodialysis), and 57.4 hours (between hemodialysis) compared with 26.2 hours in healthy volunteers. On average, approximately 20% (range: 5.6 to 35.1) of the amount of lamotrigine present in the body was eliminated by hemodialysis during a 4-hour session [see Dosage and Administration (2.1)].

Patients with Hepatic Impairment: The pharmacokinetics of lamotrigine following a single 100-mg dose of lamotrigine were evaluated in 24 subjects with mild, moderate, and severe hepatic impairment (Child-Pugh classification system) and compared with 12 subjects without hepatic impairment. The subjects with severe hepatic impairment were without ascites (n = 2) or with ascites (n = 5). The mean apparent clearances of lamotrigine in subjects with mild (n = 12), moderate (n = 5), severe without ascites (n = 2), and severe with ascites (n = 5) liver impairment were 0.30 ± 0.09, 0.24 ± 0.1, 0.21 ± 0.04, and 0.15 ± 0.09 mL/min/kg, respectively, as compared with 0.37 ± 0.1 mL/min/kg in the healthy controls. Mean half-lives of lamotrigine in subjects with mild, moderate, severe without ascites, and severe with ascites hepatic impairment were 46 ± 20, 72 ± 44, 67 ± 11, and 100 ± 48 hours, respectively, as compared with 33 ± 7 hours in healthy controls [see Dosage and Administration (2.1)].

Pediatric Patients: The pharmacokinetics of lamotrigine following a single 2-mg/kg dose were evaluated in 2 studies in pediatric subjects (n = 29 for subjects aged 10 months to 5.9 years and n = 26 for subjects aged 5 to 11 years). Forty-three subjects received concomitant therapy with other AEDs and 12 subjects received lamotrigine as monotherapy. Lamotrigine pharmacokinetic parameters for pediatric patients are summarized in Table 14.

Population pharmacokinetic analyses involving subjects aged 2 to 18 years demonstrated that lamotrigine clearance was influenced predominantly by total body weight and concurrent AED therapy. The oral clearance of lamotrigine was higher, on a body weight basis, in pediatric patients than in adults. Weight-normalized lamotrigine clearance was higher in those subjects weighing <30 kg compared with those weighing >30 kg. Accordingly, patients weighing <30 kg may need an increase of as much as 50% in maintenance doses, based on clinical response, as compared with subjects weighing >30 kg being administered the same AEDs [see Dosage and Administration (2.2)]. These analyses also revealed that, after accounting for body weight, lamotrigine clearance was not significantly influenced by age. Thus, the same weight-adjusted doses should be administered to children irrespective of differences in age. Concomitant AEDs which influence lamotrigine clearance in adults were found to have similar effects in children.

Table 14. Mean Pharmacokinetic Parameters in Pediatric Subjects with Epilepsy
Pediatric Study Population | Number of Subjects | Tmax (h) | t1/2 (h) | CL/F (mL/min/kg)
Ages 10 months to 5.3 years; Subjects taking carbamazepine, phenytoin, phenobarbital, or primidonea | 10 | 3.0 (1.0 to 5.9) | 7.7 (5.7 to 11.4) | 3.62 (2.44 to 5.28)
Subjects taking antiepileptic drugs with no known effect on the apparent clearance of lamotrigine | 7 | 5.2 (2.9 to 6.1) | 19.0 (12.9 to 27.1) | 1.2 (0.75 to 2.42)
Subjects taking valproate only | 8 | 2.9 (1.0 to 6.0) | 44.9 (29.5 to 52.5) | 0.47 (0.23 to 0.77)
Ages 5 to 11 years; Subjects taking carbamazepine, phenytoin, phenobarbital, or primidonea | 7 | 1.6 (1.0 to 3.0) | 7.0 (3.8 to 9.8) | 2.54 (1.35 to 5.58)
Subjects taking carbamazepine, phenytoin, phenobarbital, or primidonea plus valproate | 8 | 3.3 (1.0 to 6.4) | 19.1 (7.0 to 31.2) | 0.89 (0.39 to 1.93)
Subjects taking valproate onlyb | 3 | 4.5 (3.0 to 6.0) | 65.8 (50.7 to 73.7) | 0.24 (0.21 to 0.26)
Ages 13 to 18 years; Subjects taking carbamazepine, phenytoin, phenobarbital, or primidonea | 11 | ___c | ___c | 1.3
Subjects taking carbamazepine, phenytoin, phenobarbital, or primidonea plus valproate | 8 | ___c | ___c | 0.5
Subjects taking valproate only | 4 | ___c | ___c | 0.3

a Carbamazepine, phenytoin, phenobarbital, and primidone have been shown to increase the apparent clearance of lamotrigine. Estrogen-containing oral contraceptives, rifampin, and the protease inhibitors lopinavir/ritonavir and atazanavir/ritonavir have also been shown to increase the apparent clearance of lamotrigine [see Drug Interactions (7)].
b Two subjects were included in the calculation for mean Tmax.
c Parameter not estimated.

Geriatric Patients: The pharmacokinetics of lamotrigine following a single 150-mg dose of lamotrigine were evaluated in 12 elderly volunteers between the ages of 65 and 76 years (mean creatinine clearance = 61 mL/min, range: 33 to 108 mL/min). The mean half-life of lamotrigine in these subjects was 31.2 hours (range: 24.5 to 43.4 hours), and the mean clearance was 0.40 mL/min/kg (range: 0.26 to 0.48 mL/min/kg).

Male and Female Patients: The clearance of lamotrigine is not affected by gender. However, during dose escalation of lamotrigine in 1 clinical trial in patients with epilepsy on a stable dose of valproate (n = 77), mean trough lamotrigine concentrations unadjusted for weight were 24% to 45% higher (0.3 to 1.7 mcg/mL) in females than in males.

Racial or Ethnic Groups: The apparent oral clearance of lamotrigine was 25% lower in non-Caucasians than Caucasians.

13 NONCLINICAL TOXICOLOGY

13.1 Carcinogenesis, Mutagenesis, Impairment of Fertility

Carcinogenesis

No evidence of carcinogenicity was seen in mice or rats following oral administration of lamotrigine for up to 2 years at doses up to 30 mg/kg/day and 10 to 15 mg/kg/day, respectively. The highest doses tested are less than the human dose of 400 mg/day on a body surface area (mg/m^2) basis.

Mutagenesis

Lamotrigine was negative in in vitro gene mutation (Ames and mouse lymphoma tk) assays and in clastogenicity (in vitro human lymphocyte and in vivo rat bone marrow) assays.

Impairment of Fertility

No evidence of impaired fertility was detected in rats given oral doses of lamotrigine up to 20 mg/kg/day. The highest dose tested is less than the human dose of 400 mg/day on a mg/m^2 basis.

14 CLINICAL STUDIES

The efficacy of SUBVENITE for the treatment of epilepsy and bipolar disorder is based on the established effectiveness of lamotrigine oral tablet. The studies below described the effectiveness of lamotrigine oral tablet for the treatment of epilepsy and bipolar disorder. SUBVENITE (lamotrigine oral suspension) demonstrated similar bioavailability to lamotrigine oral tablet [see Clinical Pharmacology (12.3)].

14.1 Epilepsy

Monotherapy with Lamotrigine in Adults with Partial-Onset Seizures Already Receiving Treatment with Carbamazepine, Phenytoin, Phenobarbital, or Primidone as the Single Antiepileptic Drug

The effectiveness of monotherapy with lamotrigine was established in a multicenter, double-blind clinical trial enrolling 156 adult outpatients with partial-onset seizures. The patients experienced at least 4 simple partial-onset, complex partial-onset, and/or secondarily generalized seizures during each of 2 consecutive 4-week periods while receiving carbamazepine or phenytoin monotherapy during baseline. Lamotrigine (target dose of 500 mg/day) or valproate (1,000 mg/day) was added to either carbamazepine or phenytoin monotherapy over a 4-week period. Patients were then converted to monotherapy with lamotrigine or valproate during the next 4 weeks, then continued on monotherapy for an additional 12-week period.

Trial endpoints were completion of all weeks of trial treatment or meeting an escape criterion. Criteria for escape relative to baseline were: (1) doubling of average monthly seizure count, (2) doubling of highest consecutive 2-day seizure frequency, (3) emergence of a new seizure type (defined as a seizure that did not occur during the 8-week baseline) that is more severe than seizure types that occur during study treatment, or (4) clinically significant prolongation of generalized tonic-clonic seizures. The primary efficacy variable was the proportion of patients in each treatment group who met escape criteria.

The percentages of patients who met escape criteria were 42% (32/76) in the group receiving lamotrigine and 69% (55/80) in the valproate group. The difference in the percentage of patients meeting escape criteria was statistically significant (P= 0.0012) in favor of lamotrigine. No differences in efficacy based on age, sex, or race were detected.

Patients in the control group were intentionally treated with a relatively low dose of valproate; as such, the sole objective of this trial was to demonstrate the effectiveness and safety of monotherapy with lamotrigine, and cannot be interpreted to imply the superiority of lamotrigine to an adequate dose of valproate.

Adjunctive Therapy with Lamotrigine in Adults with Partial-Onset Seizures

The effectiveness of lamotrigine as adjunctive therapy (added to other AEDs) was initially established in 3 pivotal, multicenter, placebo-controlled, double-blind clinical trials in 355 adults with refractory partial-onset seizures. The patients had a history of at least 4 partial-onset seizures per month in spite of receiving 1 or more AEDs at therapeutic concentrations and in 2 of the trials were observed on their established AED regimen during baselines that varied between 8 to 12 weeks. In the third trial, patients were not observed in a prospective baseline. In patients continuing to have at least 4 seizures per month during the baseline, lamotrigine or placebo was then added to the existing therapy. In all 3 trials, change from baseline in seizure frequency was the primary measure of effectiveness. The results given below are for all partial-onset seizures in the intent-to-treat population (all patients who received at least 1 dose of treatment) in each trial, unless otherwise indicated. The median seizure frequency at baseline was 3 per week while the mean at baseline was 6.6 per week for all patients enrolled in efficacy trials.

One trial (n = 216) was a double-blind, placebo-controlled, parallel trial consisting of a 24-week treatment period. Patients could not be on more than 2 other anticonvulsants and valproate was not allowed. Patients were randomized to receive placebo, a target dose of 300 mg/day of lamotrigine, or a target dose of 500 mg/day of lamotrigine. The median reductions in the frequency of all partial-onset seizures relative to baseline were 8% in patients receiving placebo, 20% in patients receiving 300 mg/day of lamotrigine, and 36% in patients receiving 500 mg/day of lamotrigine. The seizure frequency reduction was statistically significant in the 500-mg/day group compared with the placebo group, but not in the 300-mg/day group.

A second trial (n = 98) was a double-blind, placebo-controlled, randomized, crossover trial consisting of two 14-week treatment periods (the last 2 weeks of which consisted of dose tapering) separated by a 4-week washout period. Patients could not be on more than 2 other anticonvulsants and valproate was not allowed. The target dose of lamotrigine was 400 mg/day. When the first 12 weeks of the treatment periods were analyzed, the median change in seizure frequency was a 25% reduction on lamotrigine compared with placebo (P<0.001).

The third trial (n = 41) was a double-blind, placebo-controlled, crossover trial consisting of two 12-week treatment periods separated by a 4-week washout period. Patients could not be on more than 2 other anticonvulsants. Thirteen patients were on concomitant valproate; these patients received 150 mg/day of lamotrigine. The 28 other patients had a target dose of 300 mg/day of lamotrigine. The median change in seizure frequency was a 26% reduction on lamotrigine compared with placebo (P<0.01).

No differences in efficacy based on age, sex, or race, as measured by change in seizure frequency, were detected.

Adjunctive Therapy with Lamotrigine in Pediatric Patients with Partial-Onset Seizures

The effectiveness of lamotrigine as adjunctive therapy in pediatric patients with partial-onset seizures was established in a multicenter, double-blind, placebo-controlled trial in 199 patients aged 2 to 16 years (n = 98 on lamotrigine, n = 101 on placebo). Following an 8-week baseline phase, patients were randomized to 18 weeks of treatment with lamotrigine or placebo added to their current AED regimen of up to 2 drugs. Patients were dosed based on body weight and valproate use. Target doses were designed to approximate 5 mg/kg/day for patients taking valproate (maximum dose: 250 mg/day) and 15 mg/kg/day for the patients not taking valproate (maximum dose: 750 mg/day). The primary efficacy endpoint was percentage change from baseline in all partial-onset seizures. For the intent-to-treat population, the median reduction of all partial-onset seizures was 36% in patients treated with lamotrigine and 7% on placebo, a difference that was statistically significant (P<0.01).

Adjunctive Therapy with Lamotrigine in Pediatric and Adult Patients with Lennox-Gastaut Syndrome

The effectiveness of lamotrigine as adjunctive therapy in patients with Lennox-Gastaut syndrome was established in a multicenter, double-blind, placebo-controlled trial in 169 patients aged 3 to 25 years (n = 79 on lamotrigine, n = 90 on placebo). Following a 4-week, single-blind, placebo phase, patients were randomized to 16 weeks of treatment with lamotrigine or placebo added to their current AED regimen of up to 3 drugs. Patients were dosed on a fixed-dose regimen based on body weight and valproate use. Target doses were designed to approximate 5 mg/kg/day for patients taking valproate (maximum dose: 200 mg/day) and 15 mg/kg/day for patients not taking valproate (maximum dose: 400 mg/day). The primary efficacy endpoint was percentage change from baseline in major motor seizures (atonic, tonic, major myoclonic, and tonic-clonic seizures). For the intent-to-treat population, the median reduction of major motor seizures was 32% in patients treated with lamotrigine and 9% on placebo, a difference that was statistically significant (P<0.05). Drop attacks were significantly reduced by lamotrigine (34%) compared with placebo (9%), as were tonic-clonic seizures (36% reduction versus 10% increase for lamotrigine and placebo, respectively).

Adjunctive Therapy with Lamotrigine in Pediatric and Adult Patients with Primary Generalized Tonic-Clonic Seizures

The effectiveness of lamotrigine as adjunctive therapy in patients with PGTC seizures was established in a multicenter, double-blind, placebo-controlled trial in 117 pediatric and adult patients aged 2 years and older (n = 58 on lamotrigine, n = 59 on placebo). Patients with at least 3 PGTC seizures during an 8-week baseline phase were randomized to 19 to 24 weeks of treatment with lamotrigine or placebo added to their current AED regimen of up to 2 drugs. Patients were dosed on a fixed-dose regimen, with target doses ranging from 3 to 12 mg/kg/day for pediatric patients and from 200 to 400 mg/day for adult patients based on concomitant AEDs.

The primary efficacy endpoint was percentage change from baseline in PGTC seizures. For the intent-to-treat population, the median percent reduction in PGTC seizures was 66% in patients treated with lamotrigine and 34% on placebo, a difference that was statistically significant (P = 0.006).

14.2 Bipolar Disorder

Adults

The effectiveness of lamotrigine in the maintenance treatment of bipolar I disorder was established in 2 multicenter, double-blind, placebo-controlled trials in adult patients (aged 18 to 82 years) who met DSM-IV criteria for bipolar I disorder. Trial 1 enrolled patients with a current or recent (within 60 days) depressive episode as defined by DSM-IV and Trial 2 included patients with a current or recent (within 60 days) episode of mania or hypomania as defined by DSM-IV. Both trials included a cohort of patients (30% of 404 subjects in Trial 1 and 28% of 171 patients in Trial 2) with rapid cycling bipolar disorder (4 to 6 episodes per year).

In both trials, patients were titrated to a target dose of 200 mg of lamotrigine as add-on therapy or as monotherapy with gradual withdrawal of any psychotropic medications during an 8- to 16-week open-label period. Overall, 81% of 1,305 patients participating in the open-label period were receiving 1 or more other psychotropic medications, including benzodiazepines, selective serotonin reuptake inhibitors (SSRIs), atypical antipsychotics (including olanzapine), valproate, or lithium, during titration of lamotrigine. Patients with a CGI-severity score of 3 or less maintained for at least 4 continuous weeks, including at least the final week on monotherapy with lamotrigine, were randomized to a placebo-controlled, double-blind treatment period for up to 18 months. The primary endpoint was TIME (time to intervention for a mood episode or one that was emerging, time to discontinuation for either an adverse event that was judged to be related to bipolar disorder, or for lack of efficacy). The mood episode could be depression, mania, hypomania, or a mixed episode.

In Trial 1, patients received double-blind monotherapy with lamotrigine 50 mg/day (n = 50), lamotrigine 200 mg/day (n = 124), lamotrigine 400 mg/day (n = 47), or placebo (n = 121). Lamotrigine (200- and 400-mg/day treatment groups combined) was superior to placebo in delaying the time to occurrence of a mood episode (Figure 1). Separate analyses of the 200- and 400-mg/day dose groups revealed no added benefit from the higher dose.

In Trial 2, patients received double-blind monotherapy with lamotrigine (100 to 400 mg/day, n = 59), or placebo (n = 70). Lamotrigine was superior to placebo in delaying time to occurrence of a mood episode (Figure 2). The mean dose of lamotrigine was about 211 mg/day.

Although these trials were not designed to separately evaluate time to the occurrence of depression or mania, a combined analysis for the 2 trials revealed a statistically significant benefit for lamotrigine over placebo in delaying the time to occurrence of both depression and mania, although the finding was more robust for depression.

Figure 1: Kaplan-Meier Estimation of Cumulative Proportion of Patients with Mood Episode (Trial 1)

Figure 2: Kaplan-Meier Estimation of Cumulative Proportion of Patients with Mood Episode (Trial 2)

16 HOW SUPPLIED/STORAGE AND HANDLING

16.1 How Supplied

SUBVENITE (lamotrigine) oral suspension contains 10 mg/mL lamotrigine. It is a pink, cherry-flavored suspension and is supplied in high-density polyethylene (HDPE) bottles with white, polypropylene, child-resistant closures with a foam liner and heat induction layered inner seal:

8 oz (240 mL), NDC 69102-418-01

2 x 8 oz (480mL), NDC 69102-418-02

16.2 Storage and Handling

Store at 20°C to 25°C (68°F to 77°F); excursions permitted to 15°C to 30°C (59°F to 86°F) [See USP Controlled Room Temperature].

Discard the unused portion 90 days after first opening.

17 PATIENT COUNSELING INFORMATION

Advise the patient to read the FDA-approved patient labeling (Medication Guide).

Rash

Prior to initiation of treatment with SUBVENITE, inform patients that a rash or other signs or symptoms of hypersensitivity (e.g., fever, lymphadenopathy) may herald a serious medical event and instruct them to report any such occurrence to their healthcare providers immediately [see Boxed Warning and Warnings and Precautions (5.1)].

Administration

Instruct patients or caregivers that a calibrated measuring device, such as an oral dosing syringe or oral dosing cup, should be obtained from the pharmacy to accurately measure and deliver the prescribed dose of medication. A household teaspoon or tablespoon is not an adequate measuring device.

Instruct patients to shake well before each use and to discard any unused portion 90 days after first opening the bottle.

Hemophagocytic Lymphohistiocytosis

Prior to initiation of treatment with SUBVENITE, inform patients that excessive immune activation may occur with SUBVENITE and that they should report signs or symptoms such as fever, rash, or lymphadenopathy to a healthcare provider immediately [see Warnings and Precautions (5.2)].

DRESS/Multiorgan Hypersensitivity Reactions, Blood Dyscrasias, and Organ Failure

Instruct patients and caregivers that a fever or rash associated with signs of other organ system involvement (e.g., lymphadenopathy, hepatic dysfunction) may be drug-related. SUBVENITE should be discontinued immediately if a serious hypersensitivity reaction is suspected Isolated organ failure or isolated blood dyscrasias without evidence of multiorgan hypersensitivity may also occur. Instruct patients to contact their healthcare providers immediately if they experience any signs or symptoms of these conditions [see Warnings and Precautions (5.3, 5.5)].

Cardiac Rhythm and Conduction Abnormalities

Inform patients that, due to its mechanism of action, SUBVENITE could lead to irregular or slowed heart rhythm. This risk is increased in patients with underlying cardiac disease or heart conduction problems or who are taking other medications that affect heart conduction. Patients should be made aware of and report cardiac signs or symptoms to their healthcare provider right away. Patients who develop syncope should lie down with raised legs and contact their healthcare provider [see Warnings and Precautions (5.4)].

Suicidal Thinking and Behavior

Inform patients, their caregivers, and families that AEDs, including SUBVENITE, may increase the risk of suicidal thoughts and behavior. Instruct them to be alert for the emergence or worsening of symptoms of depression, any unusual changes in mood or behavior, or the emergence of suicidal thoughts or behavior or thoughts about self-harm. Instruct them to immediately report behaviors of concern to their healthcare providers [see Warnings and Precautions (5.6)].

Worsening of Seizures

Instruct patients to notify their healthcare providers if worsening of seizure control occurs [see Warnings and Precautions (5.11)].

Central Nervous System Adverse Reactions

Inform patients that SUBVENITE may cause dizziness, somnolence, and other symptoms and signs of central nervous system depression. Accordingly, instruct them neither to drive a car nor to operate other complex machinery until they have gained sufficient experience on SUBVENITE to gauge whether or not it adversely affects their mental and/or motor performance.

Pregnancy and Lactation

Instruct patients to notify their healthcare providers if they become pregnant or intend to become pregnant during therapy and if they intend to breastfeed or are breastfeeding an infant.

Encourage patients to enroll in the NAAED Pregnancy Registry if they become pregnant. This registry is collecting information about the safety of AEDs during pregnancy. To enroll, patients can call the toll-free number 1-888-233-2334 [see Use in Specific Populations (8.1)].

Inform patients who intend to breastfeed that SUBVENITE is present in breast milk and advise them to monitor their child for potential adverse effects of this drug. Discuss the benefits and risks of continuing breastfeeding.

Use of Estrogen-Containing Products, Including Oral Contraceptives

Instruct women to notify their healthcare providers if they plan to start or stop use of oral contraceptives or other female hormonal preparations (including HRT). Starting estrogen-containing products, including oral contraceptives, may significantly decrease lamotrigine plasma levels and stopping estrogen-containing oral contraceptives (including the pill-free week) may significantly increase lamotrigine plasma levels [see Warnings and Precautions (5.9), Clinical Pharmacology (12.3)]. Also instruct women to promptly notify their healthcare providers if they experience adverse reactions or changes in menstrual pattern (e.g., break-through bleeding) while receiving SUBVENITE in combination with these medications.

Discontinuing SUBVENITE

Instruct patients to contact their healthcare providers before stopping SUBVENITE for any reason and to consult with their healthcare providers before resuming SUBVENITE Aseptic Meningitis

Inform patients that SUBVENITE may cause aseptic meningitis. Instruct them to notify their healthcare providers immediately if they develop signs and symptoms of meningitis such as headache, fever, nausea, vomiting, stiff neck, rash, abnormal sensitivity to light, myalgia, chills, confusion, or drowsiness while taking SUBVENITE.

Potential Medication Errors

To avoid a medication error of using the wrong drug or formulation, strongly advise patients to visually inspect their product to verify that it is SUBVENITE, as well as the correct formulation of lamotrigine, each time they fill their prescription [see Dosage Forms and Strengths (3.1,), How Supplied/Storage and Handling (16)].

Manufactured for:

OWP Pharmaceuticals, Inc.,
701 Warrenville Road, Suite 200, Lisle, IL 60532

Manufactured by:

DPT Laboratories, Ltd
307 E Josephine Street, San Antonio, TX 78215.

8082096
OWOSSUBOSPI0126

MEDICATION GUIDE
SUBVENITE (Sub-VE-nite)
(lamotrigine) oral suspension

What is the most important information I should know about SUBVENITE?

1. SUBVENITE may cause a serious skin rash that may cause you to be hospitalized or even cause death. There is no way to tell if a mild rash will become more serious. A serious skin rash can happen at any time during your treatment with SUBVENITE but is more likely to happen within the first 2 to 8 weeks of treatment. Children and teenagers aged between 2 and 17 years have a higher chance of getting this serious skin rash while taking SUBVENITE.
  The risk of getting a serious skin rash is higher if you:
  - take SUBVENITE while taking valproate [valproic acid or divalproex sodium (DEPAKOTE)].
  - take a higher starting dose of SUBVENITE than your healthcare provider prescribed.
  - increase your dose of SUBVENITE faster than prescribed.
  The risk of serious skin reactions may be associated with a variant in genes called HLA-B*1502 in people from Asian origin (mainly of Han Chinese and Thai origin). See, “Before taking SUBVENITE, tell your healthcare provider about all of your health conditions”.
  Call your healthcare provider right away if you have any of the following:
  - a skin rash
  - blistering or peeling of your skin
  - hives
  - painful sores in your mouth or around your eyes
  These symptoms may be the first signs of a serious skin reaction. A healthcare provider should examine you to decide if you should continue taking SUBVENITE.
2. Other serious reactions, including serious blood problems or liver problems. SUBVENITE can also cause other types of allergic reactions or serious problems that may affect organs and other parts of your body like your liver or blood cells. You may or may not have a rash with these types of reactions. Call your healthcare provider right away if you have any of these symptoms:
  - fever
  - frequent infections
  - severe muscle pain
  - swelling of your face, eyes, lips, or tongue
  - swollen lymph glands
  - unusual bruising or bleeding, looking pale
  - weakness, fatigue
  - yellowing of your skin or the white part of your eyes
  - trouble walking or seeing
  - seizures for the first time or happening more often
  - pain and/or tenderness in the area towards the top of your stomach (enlarged liver and/or spleen)
3. In patients with known heart problems, the use of SUBVENITE may lead to a fast heart beat. Call your healthcare provider right away if you:
  - have a fast, slow, or pounding heart beat
  - feel your heart skip a beat
  - have shortness of breath
  - have chest pain
  - feel lightheaded
4. Like other antiepileptic drugs, SUBVENITE may cause suicidal thoughts or actions in a very small number of people, about 1 in 500.
  Call a healthcare provider right away if you have any of these symptoms, especially if they are new, worse, or worry you:
  - thoughts about suicide or dying
  - attempt to commit suicide
  - new or worse depression
  - new or worse anxiety
  - feeling agitated or restless
  - panic attacks
  - trouble sleeping (insomnia)
  - new or worse irritability
  - acting aggressive, being angry, or violent
  - acting on dangerous impulses
  - an extreme increase in activity and talking (mania)
  - other unusual changes in behavior or mood
  Do not stop SUBVENITE without first talking to a healthcare provider.
  - Stopping SUBVENITE suddenly can cause serious problems.
  - Suicidal thoughts or actions can be caused by things other than medicines. If you have suicidal thoughts or actions, your healthcare provider may check for other causes.
  How can I watch for early symptoms of suicidal thoughts and actions in myself or a family member?
  - Pay attention to any changes, especially sudden changes, in mood, behaviors, thoughts, or feelings.
  - Keep all follow-up visits with your healthcare provider as scheduled.
  - Call your healthcare provider between visits as needed, especially if you are worried about symptoms.
5. SUBVENITE may cause aseptic meningitis, a serious inflammation of the protective membrane that covers the brain and spinal cord.
  Call your healthcare provider right away if you have any of the following symptoms:
  - headache
  - fever
  - nausea
  - vomiting
  - stiff neck
  - rash
  - unusual sensitivity to light
  - muscle pains
  - chills
  - confusion
  - drowsiness
  Meningitis has many causes other than SUBVENITE, which your doctor would check for if you developed meningitis while taking SUBVENITE.
  SUBVENITE can cause other serious side effects. For more information ask your healthcare provider or pharmacist. Tell your healthcare provider if you have any side effect that bothers you. Be sure to read the section below entitled “What are the possible side effects of SUBVENITE?”

What is SUBVENITE?

- SUBVENITE is a prescription medicine used:
  - together with other medicines to treat certain types of seizures (partial-onset seizures, primary generalized tonic-clonic seizures, generalized seizures of Lennox-Gastaut syndrome) in people aged 2 years and older.
  - alone when changing from 1 other medicine used to treat partial-onset seizures in people aged 16 years and older.
  - for the long-term treatment of bipolar I disorder to lengthen the time between mood episodes in people who have been treated for mood episodes with other medicine.
- It is not known if SUBVENITE is safe or effective in people younger than 18 years with mood episodes such as bipolar disorder or depression.
- It is not known if SUBVENITE is safe or effective when used alone as the first treatment of seizures.
- It is not known if SUBVENITE is safe or effective for people with mood episodes who have not already been treated with other medicines.

SUBVENITE should not be used for acute treatment of manic or mixed mood episodes.

Do not take SUBVENITE:

- if you have had an allergic reaction to lamotrigine or to any of the ingredients in SUBVENITE. See the end of this leaflet for a complete list of ingredients in SUBVENITE.

Before taking SUBVENITE, tell your healthcare provider about all of your health conditions, including if you:

- have had a rash or allergic reaction to another antiseizure medicine.
- are of Asian origin, have had HLA testing before, and know you are carrying the genetic variant, HLA-B*1502.
- have or have had depression, mood problems, or suicidal thoughts or behavior.
- have a history of heart problems or irregular heart beats or any of your family members have any heart problem, including genetic abnormalities.
- have had aseptic meningitis after taking SUBVENITE (lamotrigine).
- are taking estrogen-containing products, including oral contraceptives (birth control pills) or other female hormonal medicines (such as hormone replacement therapy). Do not start or stop taking birth control pills or other female hormonal medicine until you have talked with your healthcare provider. Tell your healthcare provider if you have any changes in your menstrual pattern such as breakthrough bleeding. Stopping these medicines while you are taking SUBVENITE may cause side effects (such as dizziness, lack of coordination, or double vision). Starting these medicines may lessen how well SUBVENITE works.
- are pregnant or plan to become pregnant. It is not known if SUBVENITE may harm your unborn baby. If you become pregnant while taking SUBVENITE, talk to your healthcare provider about registering with the North American Antiepileptic Drug Pregnancy Registry. You can enroll in this registry by calling 1-888-233-2334. The purpose of this registry is to collect information about the safety of antiepileptic drugs during pregnancy.
- are breastfeeding. SUBVENITE passes into breast milk and may cause side effects in a breastfed baby. If you breastfeed while taking SUBVENITE, watch your baby closely for trouble breathing, episodes of temporarily stopping breathing, sleepiness, or poor sucking. Call your baby’s healthcare provider right away if you see any of these problems. Talk to your healthcare provider about the best way to feed your baby if you take SUBVENITE.

Tell your healthcare provider about all the medicines you take, including prescription and over-the-counter medicines, vitamins, and herbal supplements. SUBVENITE and certain other medicines may interact with each other. This may cause serious side effects.
Know the medicines you take. Keep a list of them to show your healthcare provider and pharmacist when you get a new medicine.

How should I take SUBVENITE?

- Take SUBVENITE exactly as prescribed.
- Your healthcare provider may change your dose. Do not change your dose without talking to your healthcare provider.
- Check your medicine to make sure you have received SUBVENITE. Talk to your pharmacist to check that you are given the correct medicine.
- SUBVENITE may be taken with or without food.
- The pharmacy should provide you with an oral dosing syringe or dosing cup that is needed to correctly measure your dose of SUBVENITE. Do not use a household teaspoon or tablespoon.
- Shake SUBVENITE well before each dose and throw away (discard) any unused medicine 90 days after first opening.
- Do not stop taking SUBVENITE without talking to your healthcare provider. Stopping SUBVENITE suddenly may cause serious problems. For example, if you have epilepsy and you stop taking SUBVENITE suddenly, you may have seizures that do not stop. Talk with your healthcare provider about how to stop SUBVENITE slowly.
- If you miss a dose of SUBVENITE, take it as soon as you remember. If it is almost time for your next dose, skip the missed dose. Take the next dose at your regular time. Do not take 2 doses at the same time.
- If you take too much SUBVENITE, call your healthcare provider or Poison Help line at 1-800-222-1222 or go to the nearest hospital emergency room right away.
- You may not feel the full effect of SUBVENITE for several weeks.
- If you have epilepsy, tell your healthcare provider if your seizures get worse or if you have any new types of seizures.

What should I avoid while taking SUBVENITE?
Do not drive, operate machinery, or do other dangerous activities until you know how SUBVENITE affects you.

What are the possible side effects of SUBVENITE?
SUBVENITE can cause serious side effects.
See “What is the most important information I should know about SUBVENITE?”
Common side effects of SUBVENITE include:

- dizziness
- tremor
- headache
- rash
- blurred or double vision
- fever
- lack of coordination
- abdominal pain
- infections, including seasonal flu

- sleepiness
- back pain
- nausea, vomiting
- diarrhea
- tiredness
- insomnia
- dry mouth
- stuffy nose
- sore throat

These are not all the possible side effects of SUBVENITE.
Call your doctor for medical advice about side effects. You may report side effects to FDA at 1-800-FDA-1088.

How should I store SUBVENITE?

- Store SUBVENITE at room temperature between 68° to 77°F (20° to 25°C).
- Throw away (discard) any unused medicine 90 days after first opening the bottle.

Keep SUBVENITE and all medicines out of the reach of children.

General information about the safe and effective use of SUBVENITE.
Medicines are sometimes prescribed for purposes other than those listed in a Medication Guide. Do not use SUBVENITE for a condition for which it was not prescribed. Do not give SUBVENITE to other people, even if they have the same symptoms that you have. It may harm them.
If you take a urine drug screening test, SUBVENITE may make the test result positive for another drug. If you require a urine drug screening test, tell the healthcare professional administering the test that you are taking SUBVENITE.
You can ask your healthcare provider or pharmacist for information about SUBVENITE that is written for health professionals.

What are the ingredients in SUBVENITE?
Active ingredient: lamotrigine, USP.
Inactive ingredients: carboxymethylcellulose sodium, cherry flavor, FD&C Red 40, FD&C Yellow 6, glycerin, methylparaben, polyethylene glycol, propylene glycol, purified water, saccharin sodium, silicified microcrystalline cellulose, sodium benzoate, sodium phosphate dibasic, sorbitol solution, sucralose, xanthan gum.

Manufactured by:
DPT Laboratories, Ltd
307 E Josephine Street, San Antonio, TX 78215.
Manufactured for: OWP Pharmaceuticals, Inc.,
701 Warrenville Road, Suite 200, Lisle, IL 60532

8082161
OWOSSUBOSMGI0126
For more information, go to www.owppharma.com or call 1-800-273-6729.

This Medication Guide has been approved by the U.S Food and Drug Administration

Issued: 01/2026

PACKAGE LABEL.PRINCIPAL DISPLAY PANEL - 10 mg/mL

240 mL Suspension

NDC 69102-418-01

SUBVENITE

(lamotrigine) Oral Suspension, 10 mg/mL

Rx Only

Container Label

Carton Label